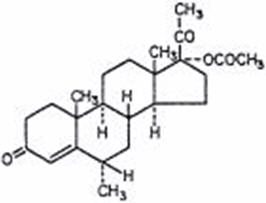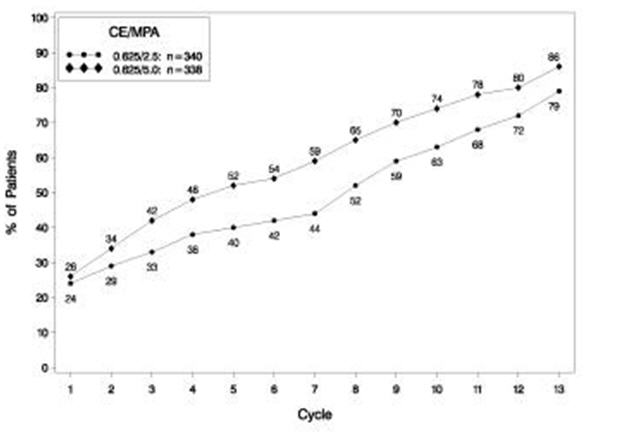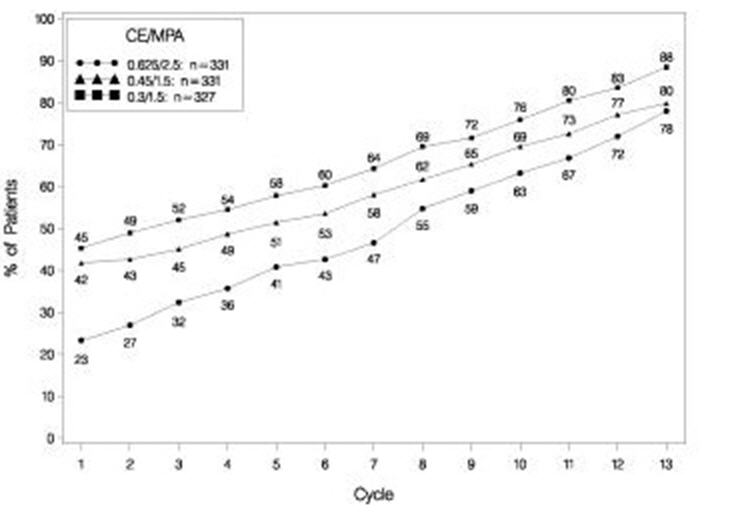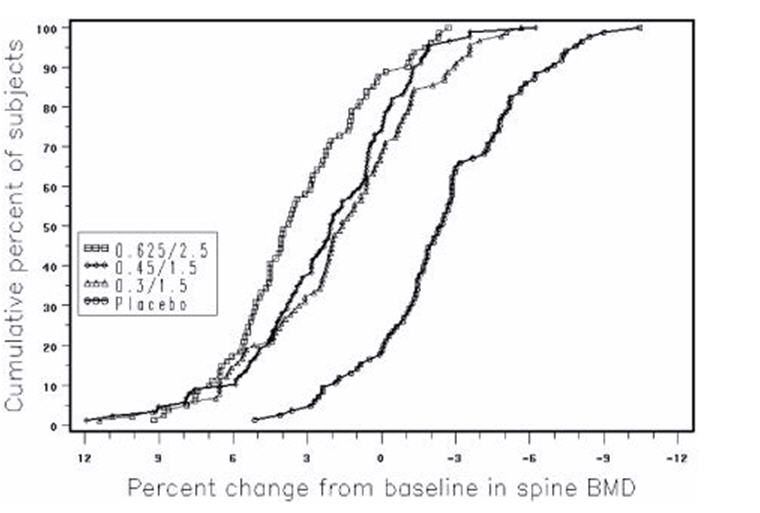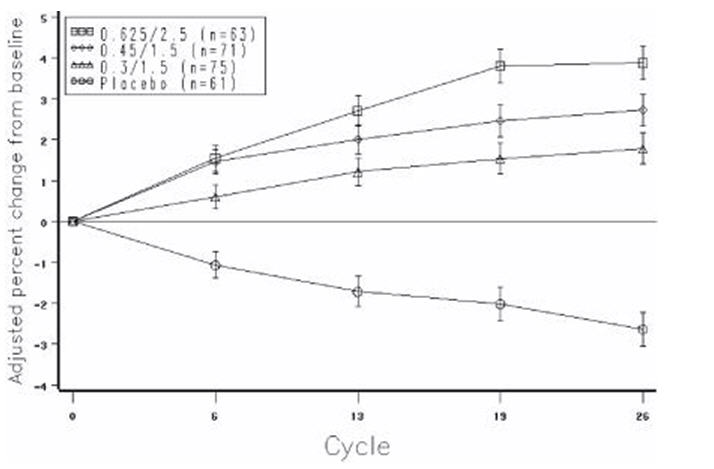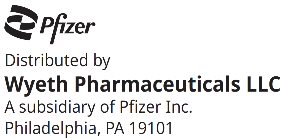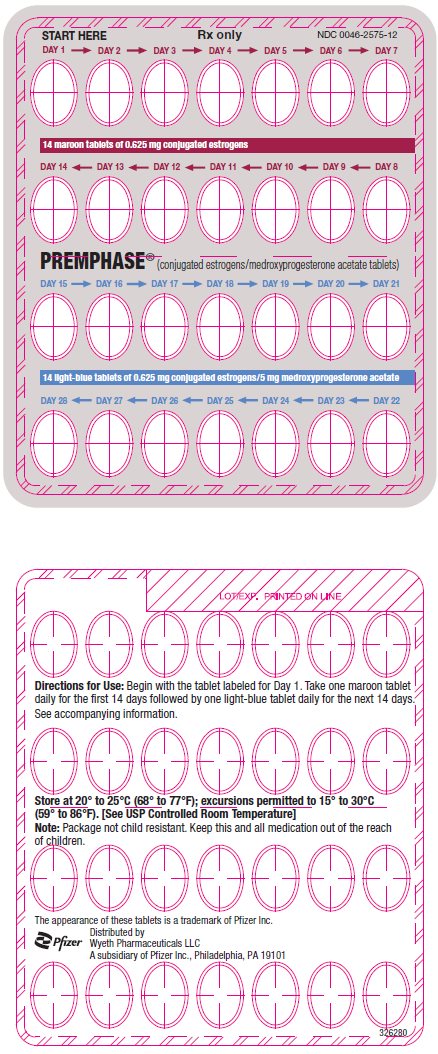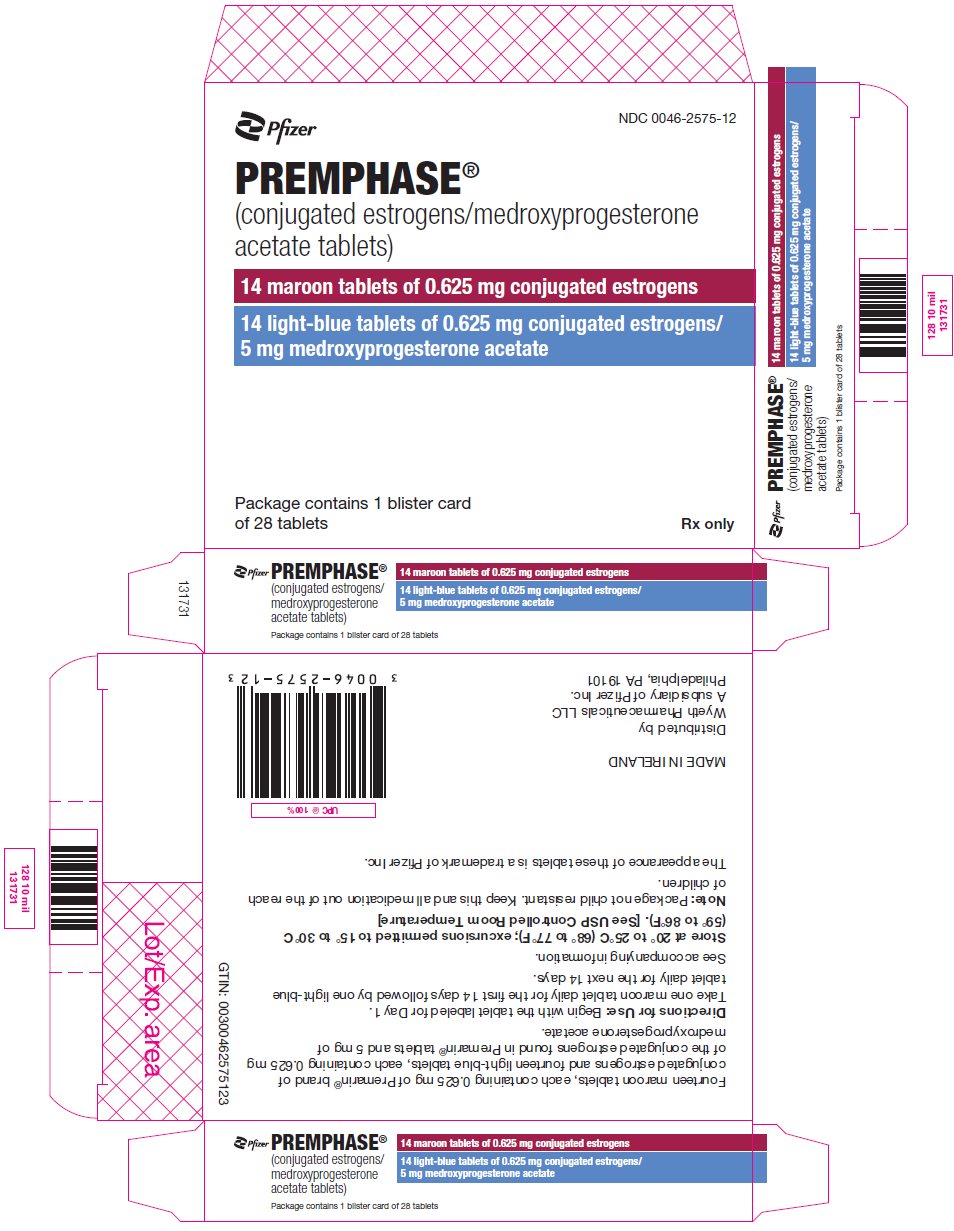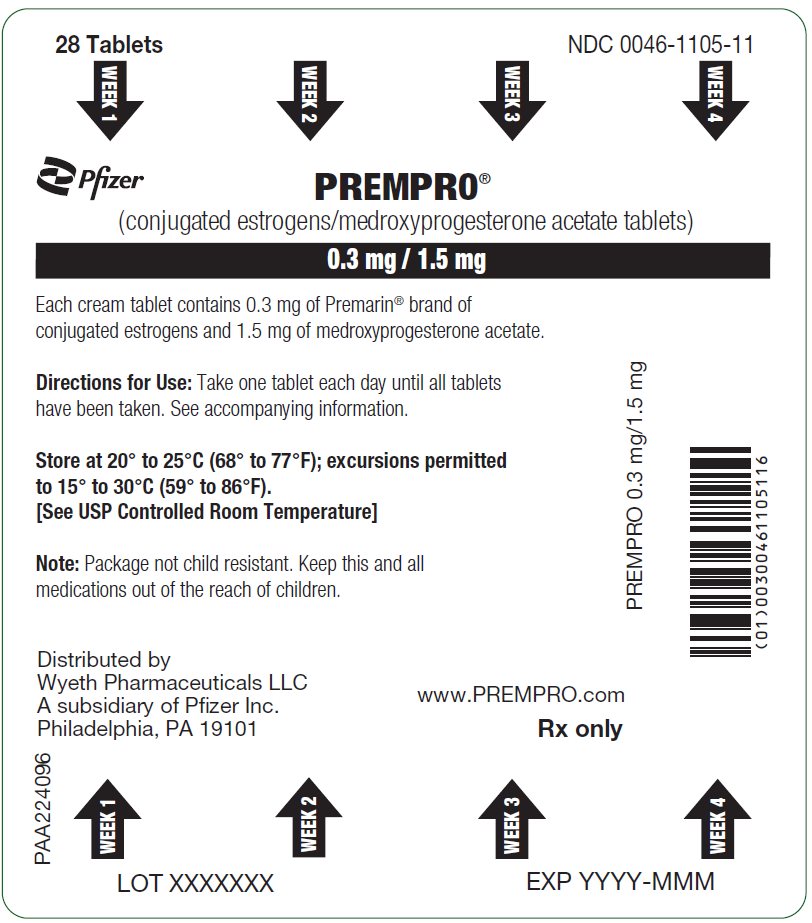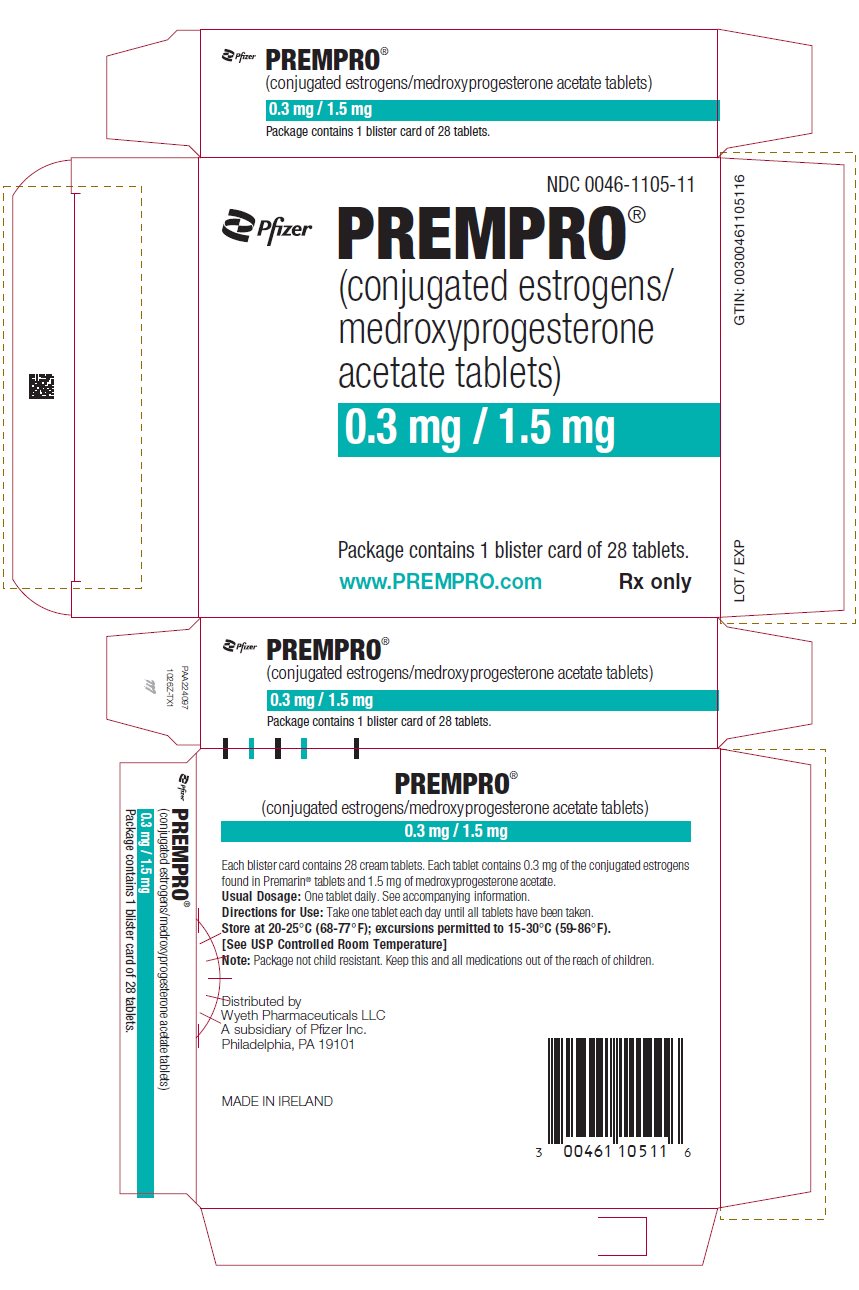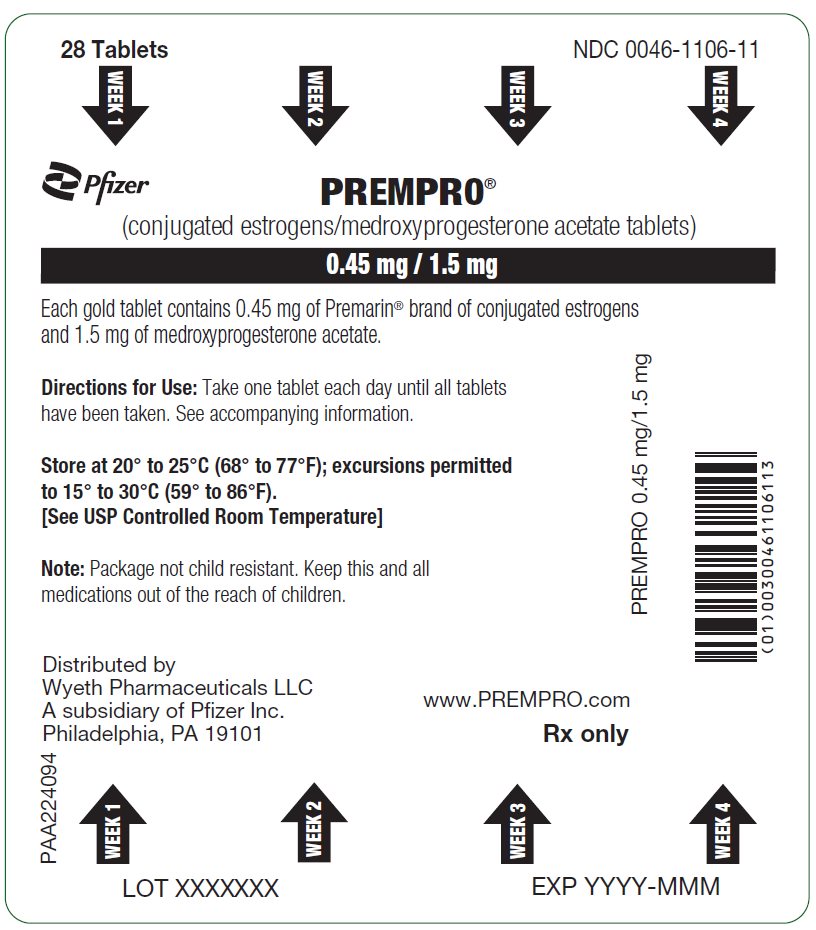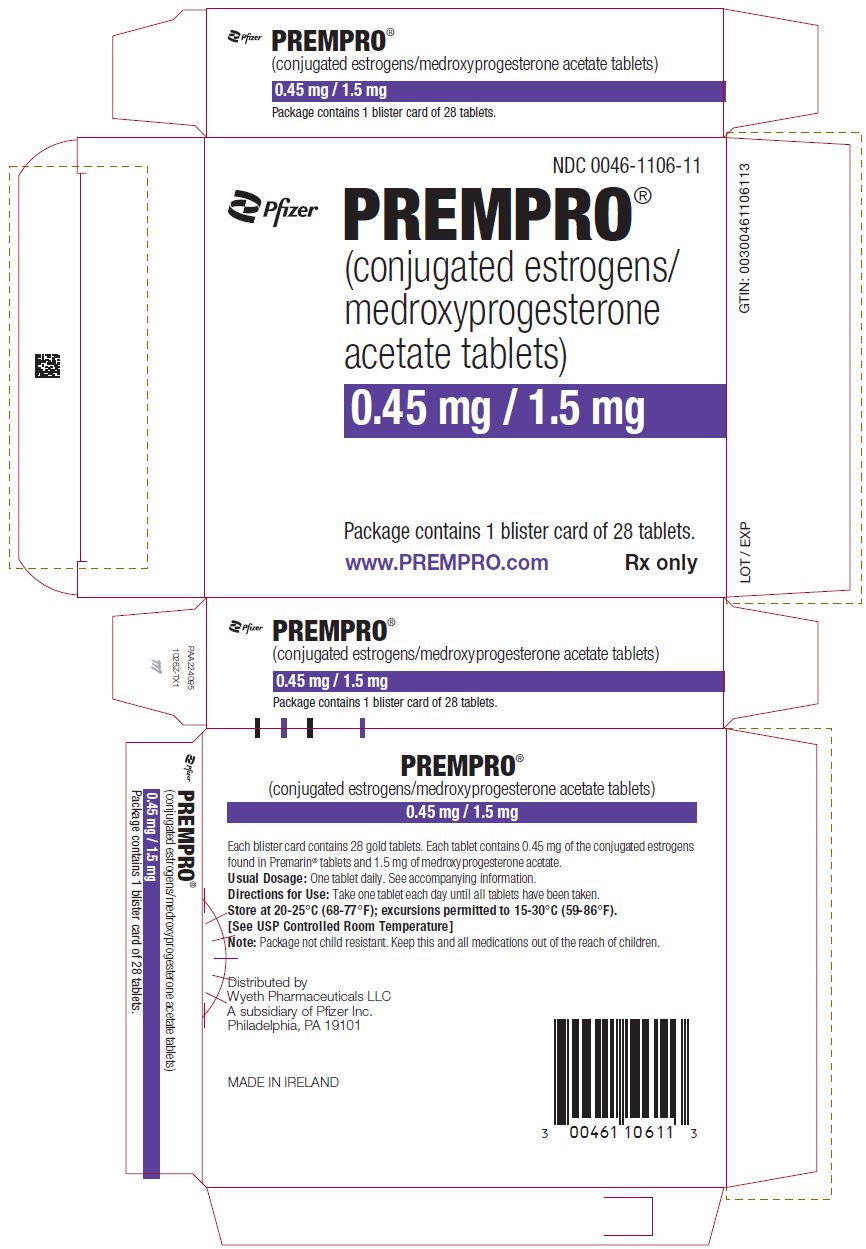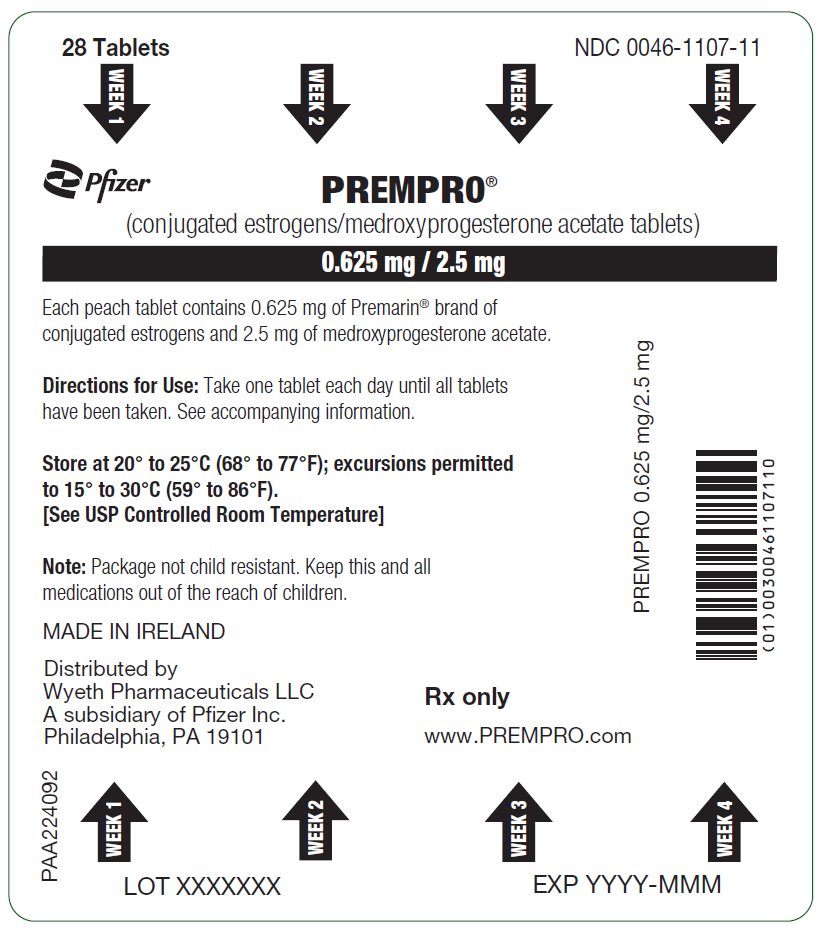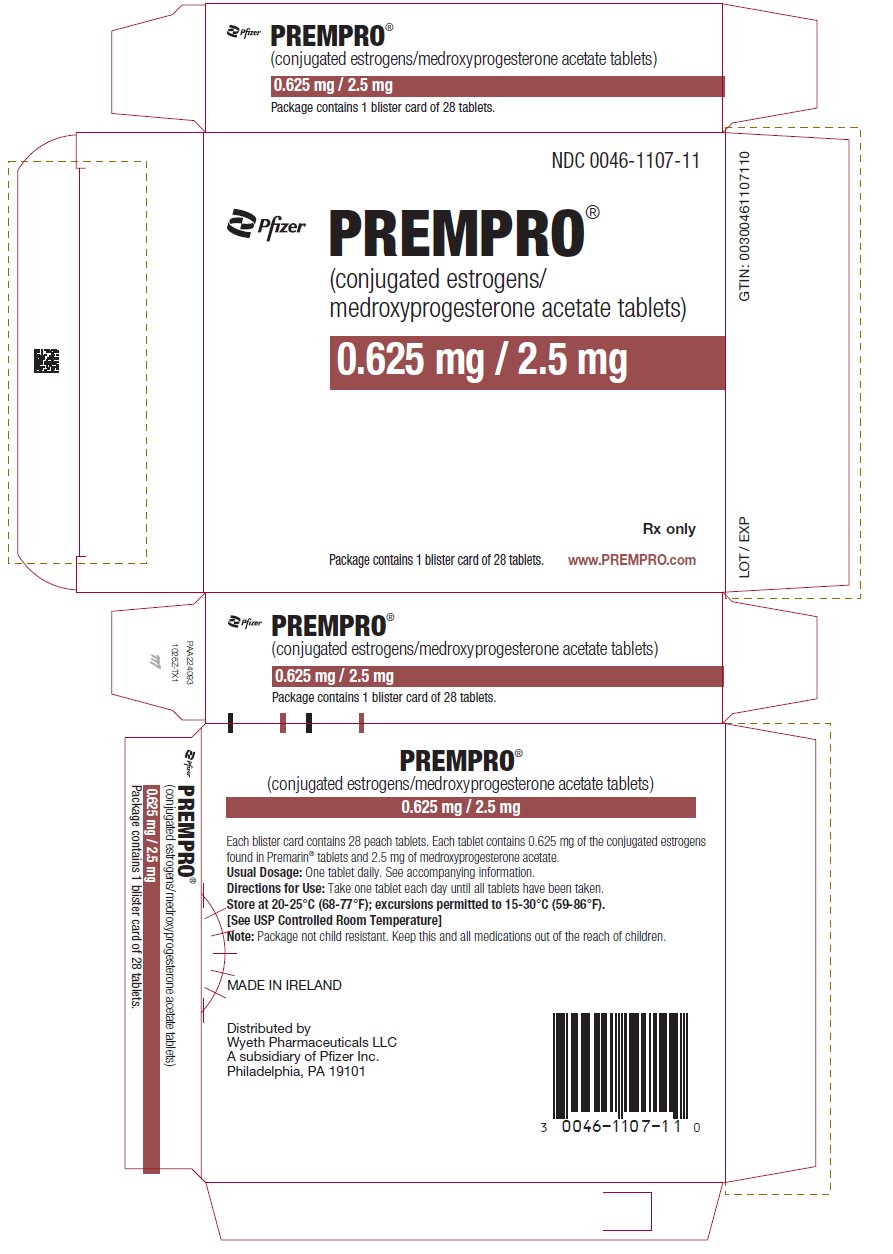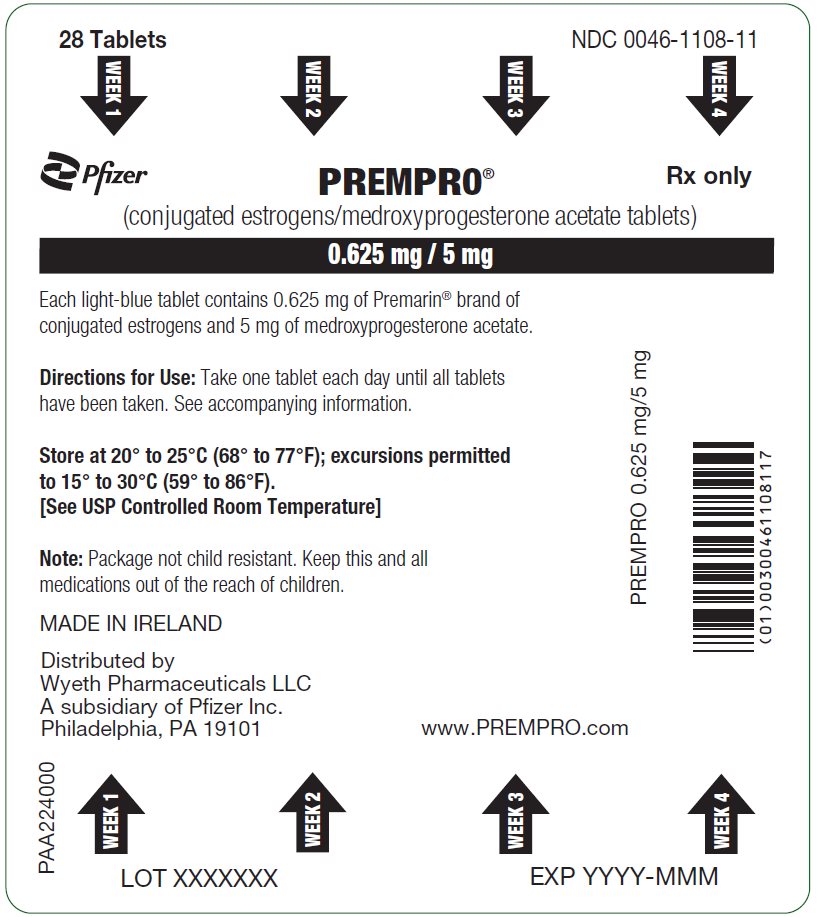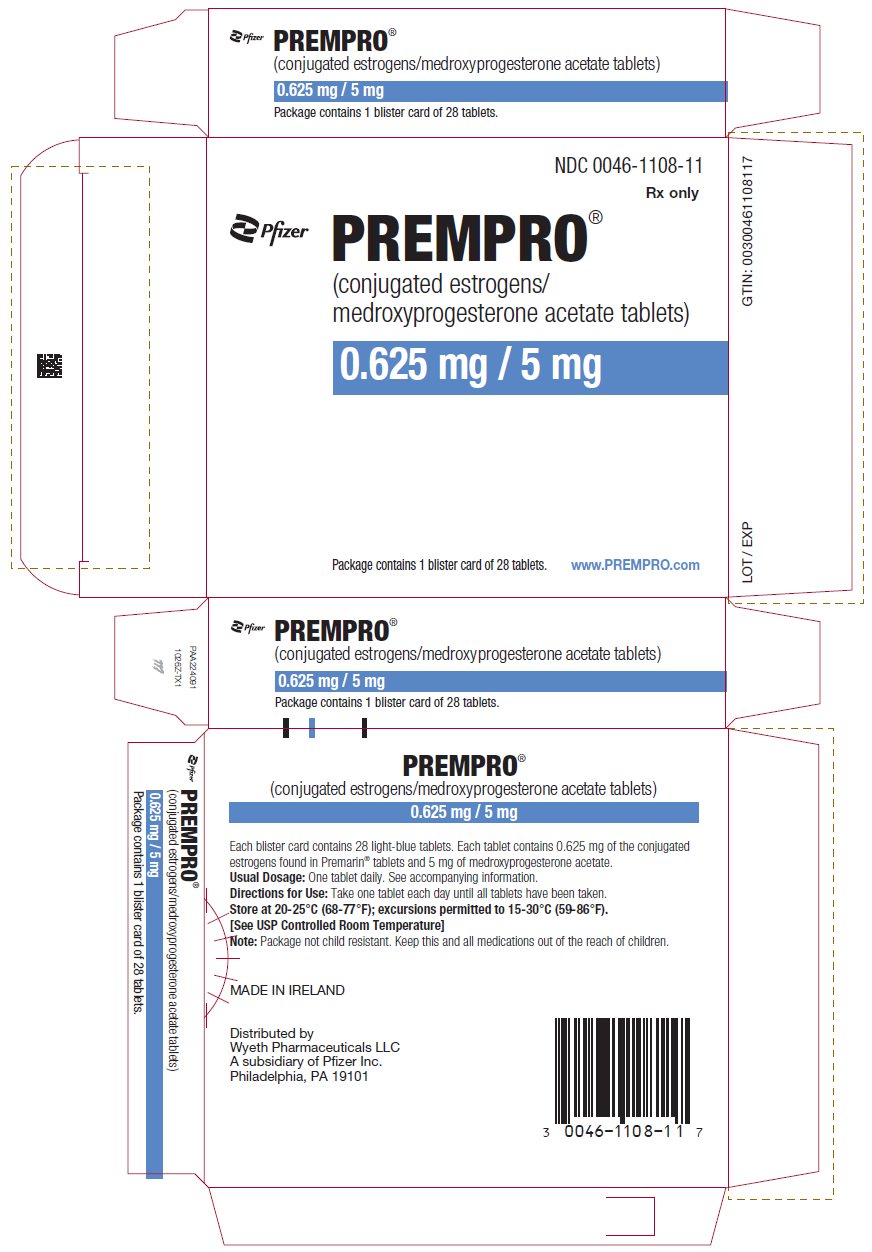 DRUG LABEL: Premphase
NDC: 0046-2575 | Form: KIT | Route: ORAL
Manufacturer: Wyeth Pharmaceuticals LLC, a subsidiary of Pfizer Inc.
Category: prescription | Type: HUMAN PRESCRIPTION DRUG LABEL
Date: 20251104

ACTIVE INGREDIENTS: ESTROGENS, CONJUGATED 0.625 mg/1 1; MEDROXYPROGESTERONE ACETATE 5 mg/1 1; ESTROGENS, CONJUGATED 0.625 mg/1 1
INACTIVE INGREDIENTS: HYDROXYPROPYL CELLULOSE (1600000 WAMW); MICROCRYSTALLINE CELLULOSE; LACTOSE MONOHYDRATE; MAGNESIUM STEARATE; POLYETHYLENE GLYCOL 400; SUCROSE; TITANIUM DIOXIDE; FD&C BLUE NO. 2; CARNAUBA WAX; TRIBASIC CALCIUM PHOSPHATE; FERROSOFERRIC OXIDE; HYPROMELLOSE 2208 (15000 MPA.S); HYPROMELLOSE 2910 (15 MPA.S); HYPROMELLOSE 2910 (6 MPA.S); METHACRYLIC ACID AND ETHYL ACRYLATE COPOLYMER; TRIETHYL CITRATE; PROPYLENE GLYCOL; HYDROXYPROPYL CELLULOSE (1600000 WAMW); MICROCRYSTALLINE CELLULOSE; LACTOSE MONOHYDRATE; MAGNESIUM STEARATE; POLYETHYLENE GLYCOL 400; SUCROSE; TITANIUM DIOXIDE; FD&C BLUE NO. 2; FD&C RED NO. 40; TRIBASIC CALCIUM PHOSPHATE; POWDERED CELLULOSE; HYPROMELLOSE 2208 (15000 MPA.S); HYPROMELLOSE 2910 (15 MPA.S); HYPROMELLOSE 2910 (6 MPA.S); CARNAUBA WAX; PROPYLENE GLYCOL

HIGHLIGHTS OF PRESCRIBING INFORMATION

These highlights do not include all the information needed to use PREMPRO/PREMPHASE safely and effectively. See full prescribing information for PREMPRO/PREMPHASE.
PREMPRO® (conjugated estrogens/medroxyprogesterone acetate tablets) PREMPHASE® (conjugated estrogens plus medroxyprogesterone acetate tablets)
Initial U.S. Approval: 1995

WARNING: CARDIOVASCULAR DISORDERS, BREAST CANCER, ENDOMETRIAL CANCER and PROBABLE DEMENTIA

See full prescribing information for complete boxed warning.

Estrogen Plus Progestin Therapy

- Estrogen plus progestin therapy should not be used for the prevention of cardiovascular disease or dementia (5.1, 5.3)
- The Women's Health Initiative (WHI) estrogen plus progestin substudy reported increased risks of stroke, deep vein thrombosis (DVT), pulmonary embolism (PE), and myocardial infarction (MI) (5.1)
- The WHI estrogen plus progestin substudy reported increased risks of invasive breast cancer (5.2)
- The WHI Memory Study (WHIMS) estrogen plus progestin ancillary study of WHI reported an increased risk of probable dementia in postmenopausal women 65 years of age and older (5.3)

Estrogen-Alone Therapy

- There is an increased risk of endometrial cancer in a woman with a uterus who uses unopposed estrogens (5.2)
- Estrogen-alone therapy should not be used for the prevention of cardiovascular disease or dementia (5.1, 5.3)
- The WHI estrogen-alone substudy reported increased risks of stroke and DVT (5.1)
- The WHIMS estrogen-alone ancillary study of WHI reported an increased risk of probable dementia in postmenopausal women 65 years of age and older (5.3)

1 INDICATIONS AND USAGE

PREMPRO/PREMPHASE is an estrogen plus progestin indicated in a woman with a uterus for:

- Treatment of Moderate to Severe Vasomotor Symptoms due to Menopause (1.1)
- Treatment of Moderate to Severe Vulvar and Vaginal Atrophy due to Menopause (1.2)
- Prevention of Postmenopausal Osteoporosis (1.3)

2 DOSAGE AND ADMINISTRATION

PREMPRO: one tablet containing conjugated estrogens (CE) plus medroxyprogesterone acetate (MPA) taken orally once daily. (2)
PREMPHASE: one maroon tablet containing 0.625 mg CE taken orally on days 1 through 14, and one light-blue tablet containing 0.625 mg CE plus 5.0 mg MPA taken orally on days 15 through 28. (2)

3 DOSAGE FORMS AND STRENGTHS

PREMPRO Tablets: 0.3 mg CE plus 1.5 mg MPA, 0.45 mg CE plus 1.5 mg MPA, 0.625 mg CE plus 2.5 mg MPA, 0.625 mg CE plus 5 mg MPA.
PREMPHASE Tablets: 0.625 mg CE, 0.625 mg CE plus 5 mg MPA.

4 CONTRAINDICATIONS

- Undiagnosed abnormal genital bleeding (4)
- Breast cancer or history of breast cancer (4, 5.2)
- Estrogen-dependent neoplasia (4, 5.2)
- Active DVT, PE, or a history of these conditions (4, 5.1)
- Active arterial thromboembolic disease (for example, stroke and MI), or a history of these conditions (4, 5.1)
- Known anaphylactic reaction or angioedema to PREMPRO/PREMPHASE (5.15, 5.16)
- Hepatic impairment or disease (4, 5.10)
- Protein C, protein S, or antithrombin deficiency, or other known thrombophilic disorders (4)

5 WARNINGS AND PRECAUTIONS

- Estrogens increase the risk of gallbladder disease (5.4)
- Discontinue estrogen if severe hypercalcemia, loss of vision, severe hypertriglyceridemia or cholestatic jaundice occurs (5.5, 5.6, 5.9, 5.10)
- Monitor thyroid function in women on thyroid replacement therapy (5.11, 5.19)

6 ADVERSE REACTIONS

In two prospective, randomized clinical studies, the most common adverse reactions >5% are abdominal pain, asthenia, back pain, headache, flatulence, nausea, depression, pruritus, breast pain, dysmenorrhea, and leukorrhea. (6.1)
To report SUSPECTED ADVERSE REACTIONS, contact Pfizer Inc. at 1-800-438-1985 or FDA at 1-800-FDA-1088 or www.fda.gov/medwatch.

7 DRUG INTERACTIONS

- Inducers and/or inhibitors of CYP3A4 may affect estrogen drug metabolism (7.1)
- Aminoglutethimide administered concomitantly with MPA may significantly depress the bioavailability of medroxyprogesterone acetate (7.1)

8 USE IN SPECIFIC POPULATIONS

- Lactation: Estrogen administration to lactating women has been shown to decrease the quantity and quality of breast milk (8.2)
- Geriatric Use: An increased risk of probable dementia in women over 65 years of age was reported in the Women's Health Initiative Memory ancillary studies of the Women's Health Initiative (5.3, 8.5)

FULL PRESCRIBING INFORMATION

WARNING: CARDIOVASCULAR DISORDERS, BREAST CANCER, ENDOMETRIAL CANCER and PROBABLE DEMENTIA

Estrogen Plus Progestin Therapy

Cardiovascular Disorders and Probable Dementia

Estrogen plus progestin therapy should not be used for the prevention of cardiovascular disease or dementia [see Warnings and Precautions (5.1, 5.3), and Clinical Studies (14.6, 14.7)].

The Women's Health Initiative (WHI) estrogen plus progestin substudy reported an increased risk of deep vein thrombosis (DVT), pulmonary embolism (PE), stroke and myocardial infarction (MI) in postmenopausal women (50 to 79 years of age) during 5.6 years of treatment with daily oral conjugated estrogen (CE) (0.625 mg) combined with medroxyprogesterone acetate (MPA) (2.5 mg), relative to placebo [see Warnings and Precautions (5.1), and Clinical Studies (14.6)].

The WHI Memory Study (WHIMS) estrogen plus progestin ancillary study of the WHI reported an increased risk of developing probable dementia in postmenopausal women 65 years of age or older during 4 years of treatment with daily CE (0.625 mg) combined with MPA (2.5 mg), relative to placebo. It is unknown whether this finding applies to younger postmenopausal women [see Warnings and Precautions (5.3), Use in Specific Populations (8.5), and Clinical Studies (14.7)].

Breast Cancer

The WHI estrogen plus progestin substudy also demonstrated an increased risk of invasive breast cancer [see Warnings and Precautions (5.2), and Clinical Studies (14.6)].

In the absence of comparable data, these risks should be assumed to be similar for other doses of CE and MPA and other combinations and dosage forms of estrogens and progestins.

Estrogens with or without progestins should be prescribed at the lowest effective doses and for the shortest duration consistent with treatment goals and risks for the individual woman.

Estrogen-Alone Therapy

Endometrial Cancer

There is an increased risk of endometrial cancer in a woman with a uterus who uses unopposed estrogens. Adding a progestin to estrogen therapy has been shown to reduce the risk of endometrial hyperplasia, which may be a precursor to endometrial cancer. Adequate diagnostic measures, including directed or random endometrial sampling when indicated, should be undertaken to rule out malignancy in postmenopausal women with undiagnosed persistent or recurring abnormal genital bleeding [see Warnings and Precautions (5.2)].

Cardiovascular Disorders and Probable Dementia

Estrogen-alone therapy should not be used for the prevention of cardiovascular disease or dementia [see Warnings and Precautions (5.1, 5.3), and Clinical Studies (14.6, 14.7)].

The WHI estrogen-alone substudy reported increased risks of stroke and DVT in postmenopausal women (50 to 79 years of age) during 7.1 years of treatment with daily oral CE (0.625 mg)-alone, relative to placebo [see Warnings and Precautions (5.1), and Clinical Studies (14.6)].

The WHIMS estrogen-alone ancillary study of WHI reported an increased risk of developing probable dementia in postmenopausal women 65 years of age or older during 5.2 years of treatment with daily CE (0.625 mg)-alone, relative to placebo. It is unknown whether this finding applies to younger postmenopausal women [see Warnings and Precautions (5.3), Use in Specific Populations (8.5), and Clinical Studies (14.7)].

In the absence of comparable data, these risks should be assumed to be similar for other doses of CE and other dosage forms of estrogens.

Estrogens with or without progestins should be prescribed at the lowest effective doses and for the shortest duration consistent with treatment goals and risks for the individual woman.

2 DOSAGE AND ADMINISTRATION

Use of estrogen-alone, or in combination with a progestin, should be with the lowest effective dose and for the shortest duration consistent with treatment goals and risks for the individual woman. Postmenopausal women should be re-evaluated periodically as clinically appropriate to determine if treatment is still necessary.

2.1 Treatment of Moderate to Severe Vasomotor Symptoms due to Menopause

PREMPRO therapy consists of a single tablet to be taken orally once daily.

PREMPHASE therapy consists of two separate tablets: one maroon 0.625 mg Premarin [conjugated estrogens (CE)] tablet taken daily on days 1 through 14 and one light-blue tablet containing 0.625 mg CE and 5 mg of medroxyprogesterone acetate (MPA) taken on days 15 through 28.

2.2 Treatment of Moderate to Severe Vulvar and Vaginal Atrophy due to Menopause

PREMPRO therapy consists of a single tablet to be taken orally once daily.

PREMPHASE therapy consists of two separate tablets: one maroon 0.625 mg CE tablet taken daily on days 1 through 14 and one light-blue tablet containing 0.625 mg CE and 5 mg MPA taken on days 15 through 28.

When prescribing solely for the treatment of moderate to severe vulvar and vaginal atrophy, topical vaginal products should be considered.

2.3 Prevention of Postmenopausal Osteoporosis

PREMPRO therapy consists of a single tablet to be taken orally once daily.

PREMPHASE therapy consists of two separate tablets: one maroon 0.625 mg CE tablet taken daily on days 1 through 14 and one light-blue tablet containing 0.625 mg CE and 5 mg of MPA taken on days 15 through 28.

When prescribing solely for the prevention of postmenopausal osteoporosis, therapy should only be considered for women at significant risk of osteoporosis and non-estrogen medications should be carefully considered.

3 DOSAGE FORMS AND STRENGTHS

PREMPRO (conjugated estrogens/medroxyprogesterone acetate tablets)
Tablet Strength | Tablet Shape/Color | Imprint
0.3 mg CE plus 1.5 mg MPA | oval/cream | PREMPRO 0.3/1.5
0.45 mg CE plus 1.5 mg MPA | oval/gold | PREMPRO 0.45/1.5
0.625 mg CE plus 2.5 mg MPA | oval/peach | PREMPRO 0.625/2.5
0.625 mg CE plus 5 mg MPA | oval/light blue | PREMPRO 0.625/5
PREMPHASE (conjugated estrogens/medroxyprogesterone acetate tablets)
Tablet Strength | Tablet Shape/Color | Imprint
0.625 mg CE | oval/maroon (14 tablets) | PREMARIN 0.625
0.625 mg CE plus 5 mg MPA | oval/light-blue (14 tablets) | PREMPRO 0.625/5

4 CONTRAINDICATIONS

PREMPRO and PREMPHASE are contraindicated in women with any of the following conditions:

- Undiagnosed abnormal genital bleeding [see Warnings and Precautions (5.2)]
- Breast cancer or a history of breast cancer [see Warnings and Precautions (5.2)]
- Estrogen-dependent neoplasia [see Warnings and Precautions (5.2)]
- Active DVT, PE, or a history of these conditions [see Warnings and Precautions (5.1)]
- Active arterial thromboembolic disease (for example, stroke and MI), or a history of these conditions [see Warnings and Precautions (5.1)]
- Known anaphylactic reaction or angioedema with PREMPRO/PREMPHASE [see Warnings and Precautions (5.15, 5.16)]
- Hepatic impairment or disease [see Warnings and Precautions (5.10)]
- Protein C, protein S, or antithrombin deficiency, or other known thrombophilic disorders

5 WARNINGS AND PRECAUTIONS

5.1 Cardiovascular Disorders

An increased risk of PE, DVT, stroke and MI has been reported with estrogen plus progestin therapy. An increased risk of stroke and DVT has been reported with estrogen-alone therapy. Should any of these occur or be suspected, estrogen with or without progestin therapy should be discontinued immediately.

Risk factors for arterial vascular disease (for example, hypertension, diabetes mellitus, tobacco use, hypercholesterolemia, and obesity) and/or venous thromboembolism (VTE) (for example, personal history or family history of VTE, obesity, and systemic lupus erythematosus) should be managed appropriately.

Stroke

In the WHI estrogen plus progestin substudy, a statistically significant increased risk of stroke was reported in women 50 to 79 years of age receiving daily CE (0.625 mg) plus MPA (2.5 mg) compared to women in the same age group receiving placebo (33 versus 25 per 10,000 women-years) [see Clinical Studies (14.6)]. The increase in risk was demonstrated after the first year and persisted.^1 Should a stroke occur or be suspected, estrogen plus progestin therapy should be discontinued immediately.

In the WHI estrogen-alone substudy, a statistically significant increased risk of stroke was reported in women 50 to 79 years of age receiving daily CE (0.625 mg)-alone compared to women in the same age group receiving placebo (45 versus 33 per 10,000 women-years). The increase in risk was demonstrated in Year 1 and persisted [see Clinical Studies (14.6)]. Should a stroke occur or be suspected, estrogen-alone therapy should be discontinued immediately.

Subgroup analyses of women 50 to 59 years of age suggest no increased risk of stroke for those women receiving CE (0.625 mg)-alone versus those receiving placebo (18 versus 21 per 10,000 women-years).^1

Coronary Heart Disease

In the WHI estrogen plus progestin substudy, there was a statistically non-significant increased risk of coronary heart disease (CHD) events (defined as nonfatal MI, silent MI, or CHD death) reported in women receiving daily CE (0.625 mg) plus MPA (2.5 mg) compared to women receiving placebo (41 versus 34 per 10,000 women-years).^1 An increase in relative risk was demonstrated in year 1, and a trend toward decreasing relative risk was reported in years 2 through 5 [see Clinical Studies (14.6)].

In the WHI estrogen-alone substudy, no overall effect on CHD events was reported in women receiving estrogen-alone compared to placebo^2 [see Clinical Studies (14.6)].

Subgroup analyses of women 50 to 59 years of age suggest a statistically non-significant reduction in CHD events (CE [0.625 mg]-alone compared to placebo) in women with less than 10 years since menopause (8 versus 16 per 10,000 women-years).^1

In postmenopausal women with documented heart disease (n = 2,763), average 66.7 years of age, in a controlled clinical trial of secondary prevention of cardiovascular disease (Heart and Estrogen/Progestin Replacement Study [HERS]), treatment with daily CE (0.625 mg) plus MPA (2.5 mg) demonstrated no cardiovascular benefit. During an average follow-up of 4.1 years, treatment with CE plus MPA did not reduce the overall rate of CHD events in postmenopausal women with established coronary heart disease. There were more CHD events in the CE plus MPA-treated group than in the placebo group in Year 1, but not during subsequent years. Two thousand, three hundred and twenty-one (2,321) women from the original HERS trial agreed to participate in an open label extension of HERS, HERS II. Average follow-up in HERS II was an additional 2.7 years, for a total of 6.8 years overall. Rates of CHD events were comparable among women in the CE plus MPA group and the placebo group in HERS, HERS II, and overall.

Venous Thromboembolism (VTE)

In the WHI estrogen plus progestin substudy, a statistically significant 2-fold greater rate of VTE (DVT and PE) was reported in women receiving daily CE (0.625 mg) plus MPA (2.5 mg) compared to women receiving placebo (35 versus 17 per 10,000 women-years). Statistically significant increases in risk for both DVT (26 versus 13 per 10,000 women-years) and PE (18 versus 8 per 10,000 women-years) were also demonstrated. The increase in VTE risk was demonstrated during the first year and persisted^3 [see Clinical Studies (14.6)]. Should a VTE occur or be suspected, estrogen plus progestin therapy should be discontinued immediately.

In the WHI estrogen-alone substudy, the risk of VTE was increased for women receiving daily CE (0.625 mg)-alone compared to placebo (30 versus 22 per 10,000 women-years), although only the increased risk of DVT reached statistical significance (23 versus 15 per 10,000 women-years). The increase in VTE risk was demonstrated during the first 2 years^4 [see Clinical Studies (14.6)]. Should a VTE occur or be suspected, estrogen-alone therapy should be discontinued immediately.

If feasible, estrogens should be discontinued at least 4 to 6 weeks before surgery of the type associated with an increased risk of thromboembolism, or during periods of prolonged immobilization.

5.2 Malignant Neoplasms

Breast Cancer

The WHI substudy of daily CE (0.625 mg)-alone provided information about breast cancer in estrogen-alone users. In the WHI estrogen-alone substudy, after an average follow-up of 7.1 years, daily CE (0.625 mg)-alone was not associated with an increased risk of invasive breast cancer [relative risk (RR) 0.80]^5 [see Clinical Studies (14.6)].

After a mean follow-up of 5.6 years, the estrogen plus progestin substudy reported an increased risk of invasive breast cancer in women who took daily CE plus MPA. In this substudy, prior use of estrogen-alone or estrogen plus progestin therapy was reported by 26% of the women. The relative risk of invasive breast cancer was 1.24, and the absolute risk was 41 versus 33 cases per 10,000 women-years, for CE plus MPA compared with placebo. Among women who reported prior use of hormone therapy, the relative risk of invasive breast cancer was 1.86, and the absolute risk was 46 versus 25 cases per 10,000 women-years, for CE plus MPA compared with placebo. Among women who reported no prior use of hormone therapy, the relative risk of invasive breast cancer was 1.09, and the absolute risk was 40 versus 36 cases per 10,000 women-years, for CE plus MPA compared with placebo. In the same substudy, invasive breast cancers were larger, were more likely to be node positive, and were diagnosed at a more advanced stage in the CE (0.625 mg) plus MPA (2.5 mg) group compared with the placebo group. Metastatic disease was rare, with no apparent difference between the two groups. Other prognostic factors, such as histologic subtype, grade and hormone receptor status did not differ between the groups^6 [see Clinical Studies (14.6)].

Consistent with the WHI clinical trials, observational studies have also reported an increased risk of breast cancer for estrogen plus progestin therapy and a smaller increased risk for estrogen-alone therapy, after several years of use. One large meta-analysis of prospective cohort studies reported increased risks that were dependent upon duration of use and could last up to > 10 years after discontinuation of estrogen plus progestin therapy and estrogen-alone therapy. Extension of the WHI trials also demonstrated increased breast cancer risk associated with estrogen plus progestin therapy. Observational studies also suggest that the risk of breast cancer was greater, and became apparent earlier, with estrogen plus progestin therapy as compared to the risk with estrogen-alone therapy. However, these studies have not found significant variation in the risk of breast cancer among different estrogen plus progestin combinations, doses, or routes of administration.

The use of estrogen-alone and estrogen plus progestin has been reported to result in an increase in abnormal mammograms requiring further evaluation.

All women should receive yearly breast examinations by a healthcare provider and perform monthly breast self-examinations. In addition, mammography examinations should be scheduled based on patient age, risk factors, and prior mammogram results.

Endometrial Cancer

Endometrial hyperplasia (a possible precursor of endometrial cancer) has been reported to occur at a rate of approximately 1% or less with PREMPRO or PREMPHASE.

An increased risk of endometrial cancer has been reported with the use of unopposed estrogen therapy in a woman with a uterus. The reported endometrial cancer risk among unopposed estrogen users is about 2 to 12 times greater than in non-users, and appears dependent on duration of treatment and on estrogen dose. Most studies show no significant increased risk associated with use of estrogens for less than 1 year. The greatest risk appears to be associated with prolonged use, with increased risks of 15- to 24-fold for 5 to 10 years or more, and this risk has been shown to persist for at least 8 to 15 years after estrogen therapy is discontinued.

Clinical surveillance of all women using estrogen-alone or estrogen plus progestin therapy is important. Adequate diagnostic measures, including directed or random endometrial sampling when indicated, should be undertaken to rule out malignancy in postmenopausal women with undiagnosed persistent or recurring abnormal genital bleeding.

There is no evidence that the use of natural estrogens results in a different endometrial risk profile than synthetic estrogens of equivalent estrogen dose. Adding a progestin to estrogen therapy in postmenopausal women has been shown to reduce the risk of endometrial hyperplasia, which may be a precursor to endometrial cancer.

Ovarian Cancer

The WHI estrogen plus progestin substudy reported a statistically non-significant increased risk of ovarian cancer. After an average follow-up of 5.6 years, the relative risk for ovarian cancer for CE plus MPA versus placebo was 1.58 (95% confidence interval (CI), 0.77–3.24). The absolute risk for CE plus MPA versus placebo was 4 versus 3 cases per 10,000 women-years.^7

A meta-analysis of 17 prospective and 35 retrospective epidemiology studies found that women who used hormonal therapy for menopausal symptoms had an increased risk for ovarian cancer. The primary analysis, using case-control comparisons, included 12,110 cancer cases from the 17 prospective studies. The relative risks associated with current use of hormonal therapy was 1.41 (95% CI 1.32 to 1.50); there was no difference in the risk estimates by duration of the exposure (less than 5 years [median of 3 years] vs. greater than 5 years [median of 10 years] of use before the cancer diagnosis). The relative risk associated with combined current and recent use (discontinued use within 5 years before cancer diagnosis) was 1.37 (95% CI 1.27–1.48), and the elevated risk was significant for both estrogen-alone and estrogen plus progestin products. The exact duration of hormone therapy use associated with an increased risk of ovarian cancer, however, is unknown.

5.3 Probable Dementia

In the WHIMS estrogen plus progestin ancillary study of WHI, a population of 4,532 postmenopausal women 65 to 79 years of age was randomized to daily CE (0.625 mg) plus MPA (2.5 mg) or placebo.

After an average follow-up of 4 years, 40 women in the CE plus MPA group and 21 women in the placebo group were diagnosed with probable dementia. The relative risk of probable dementia for CE plus MPA versus placebo was 2.05 (95% CI, 1.21–3.48). The absolute risk of probable dementia for CE plus MPA versus placebo was 45 versus 22 cases per 10,000 women-years^8 [see Use in Specific Populations (8.5), and Clinical Studies (14.7)].

In the WHIMS estrogen-alone ancillary study of WHI, a population of 2,947 hysterectomized women 65 to 79 years of age was randomized to daily CE (0.625 mg)-alone or placebo. After an average follow-up of 5.2 years, 28 women in the estrogen-alone group and 19 women in the placebo group were diagnosed with probable dementia. The relative risk of probable dementia for CE-alone versus placebo was 1.49 (95% CI, 0.83–2.66). The absolute risk of probable dementia for CE-alone versus placebo was 37 versus 25 cases per 10,000 women-years^8 [see Use in Specific Populations (8.5), and Clinical Studies (14.7)].

When data from the two populations in the WHIMS estrogen-alone and estrogen plus progestin ancillary studies were pooled as planned in the WHIMS protocol, the reported overall relative risk for probable dementia was 1.76 (95% CI, 1.19–2.60). Since both substudies were conducted in women 65 to 79 years of age, it is unknown whether these findings apply to younger postmenopausal women^8 [see Use in Specific Populations (8.5), and Clinical Studies (14.7)].

5.4 Gallbladder Disease

A 2- to 4-fold increase in the risk of gallbladder disease requiring surgery in postmenopausal women receiving estrogens has been reported.

5.5 Hypercalcemia

Estrogen administration may lead to severe hypercalcemia in women with breast cancer and bone metastases. If hypercalcemia occurs, use of the drug should be stopped and appropriate measures taken to reduce the serum calcium level.

5.6 Visual Abnormalities

Retinal vascular thrombosis has been reported in women receiving estrogens. Discontinue medication pending examination if there is sudden partial or complete loss of vision, or a sudden onset of proptosis, diplopia, or migraine. If examination reveals papilledema or retinal vascular lesions, estrogens should be permanently discontinued.

5.7 Addition of a Progestin When a Woman Has Not Had a Hysterectomy

Studies of the addition of a progestin for 10 or more days of a cycle of estrogen administration or daily with estrogen in a continuous regimen, have reported a lowered incidence of endometrial hyperplasia than would be induced by estrogen treatment alone. Endometrial hyperplasia may be a precursor to endometrial cancer.

There are, however, possible risks that may be associated with the use of progestins with estrogens compared to estrogen-alone regimens. These include an increased risk of breast cancer.

5.8 Elevated Blood Pressure

In a small number of case reports, substantial increases in blood pressure have been attributed to idiosyncratic reactions to estrogens. In a large, randomized, placebo-controlled clinical trial, a generalized effect of estrogen therapy on blood pressure was not seen.

5.9 Exacerbation of Hypertriglyceridemia

In women with pre-existing hypertriglyceridemia, estrogen therapy may be associated with elevations of plasma triglycerides leading to pancreatitis. Consider discontinuation of treatment if pancreatitis occurs.

5.10 Hepatic Impairment and/or Past History of Cholestatic Jaundice

Estrogens may be poorly metabolized in women with impaired liver function. For women with a history of cholestatic jaundice associated with past estrogen use or with pregnancy, caution should be exercised, and in the case of recurrence, medication should be discontinued.

5.11 Exacerbation of Hypothyroidism

Estrogen administration leads to increased thyroid-binding globulin (TBG) levels. Women with normal thyroid function can compensate for the increased TBG by making more thyroid hormone, thus maintaining free T4 and T3 serum concentrations in the normal range. Women dependent on thyroid hormone replacement therapy who are also receiving estrogens may require increased doses of their thyroid replacement therapy. These women should have their thyroid function monitored in order to maintain their free thyroid hormone levels in an acceptable range.

5.12 Fluid Retention

Estrogens plus progestins may cause some degree of fluid retention. Women with conditions that might be influenced by this factor, such as a cardiac or renal dysfunction, warrant careful observation when estrogens plus progestins are prescribed.

5.13 Hypocalcemia

Estrogen therapy should be used with caution in women with hypoparathyroidism as estrogen-induced hypocalcemia may occur.

5.14 Exacerbation of Endometriosis

A few cases of malignant transformation of residual endometrial implants have been reported in women treated post-hysterectomy with estrogen-alone therapy. For women known to have residual endometriosis post-hysterectomy, the addition of progestin should be considered.

5.15 Anaphylactic Reaction and Angioedema

Cases of anaphylaxis, which developed within minutes to hours after taking PREMPRO or PREMPHASE and require emergency medical management, have been reported in the postmarketing setting. Skin (hives, pruritis, swollen lips-tongue-face) and either respiratory tract (respiratory compromise) or gastrointestinal tract (abdominal pain, vomiting) involvement has been noted.

Angioedema involving the tongue, larynx, face, hands, and feet requiring medical intervention has occurred postmarketing in patients taking PREMPRO or PREMPHASE. If angioedema involves the tongue, glottis, or larynx, airway obstruction may occur. Patients who develop an anaphylactic reaction with or without angioedema after treatment with PREMPRO or PREMPHASE should not receive PREMPRO or PREMPHASE again.

5.16 Hereditary Angioedema

Exogenous estrogens may exacerbate symptoms of angioedema in women with hereditary angioedema.

5.17 Exacerbation of Other Conditions

Estrogen therapy may cause an exacerbation of asthma, diabetes mellitus, epilepsy, migraine, porphyria, systemic lupus erythematosus, and hepatic hemangiomas and should be used with caution in women with these conditions.

5.18 Laboratory Tests

Serum follicle stimulating hormone (FSH) and estradiol levels have not been shown to be useful in the management of moderate to severe vasomotor symptoms and moderate to severe symptoms of vulvar and vaginal atrophy.

5.19 Drug-Laboratory Test Interactions

- Accelerated prothrombin time, partial thromboplastin time, and platelet aggregation time; increased platelet count; increased factors II, VII antigen, VIII antigen, VIII coagulant activity, IX, X, XII, VII-X complex, II-VII-X complex, and beta-thromboglobulin; decreased levels of anti-factor Xa and antithrombin III, decreased antithrombin III activity; increased levels of fibrinogen and fibrinogen activity; increased plasminogen antigen and activity.
- Increased thyroid-binding globulin (TBG) leading to increased circulating total thyroid hormone, as measured by protein-bound iodine (PBI), T4 levels (by column or by radioimmunoassay), or T3 levels by radioimmunoassay. T3 resin uptake is decreased, reflecting the elevated TBG. Free T4 and free T3 concentrations are unaltered. Women on thyroid replacement therapy may require higher doses of thyroid hormone.
- Other binding proteins may be elevated in serum, for example, corticosteroid binding globulin (CBG), sex hormone-binding globulin (SHBG), leading to increased total circulating corticosteroids and sex steroids, respectively. Free hormone concentrations, such as testosterone and estradiol, may be decreased. Other plasma proteins may be increased (angiotensinogen/renin substrate, alpha-1-antitrypsin, ceruloplasmin).
- Increased plasma high-density lipoprotein (HDL) and HDL2 cholesterol subfraction, reduced low-density lipoprotein (LDL) cholesterol, increased triglyceride levels.
- Impaired glucose tolerance.

6 ADVERSE REACTIONS

The following serious adverse reactions are discussed elsewhere in the labeling:

- Cardiovascular Disorders [see Boxed Warning, Warnings and Precautions (5.1)]
- Malignant Neoplasms [see Boxed Warning, Warnings and Precautions (5.2)]

6.1 Clinical Trials Experience

Because clinical trials are conducted under widely varying conditions, adverse reaction rates observed in the clinical trial of a drug cannot be directly compared to rates in the clinical trials of another drug and may not reflect the rates observed in practice.

In a 1-year clinical trial that included 678 postmenopausal women treated with PREMPRO and 351 postmenopausal women treated with PREMPHASE, the following adverse reactions occurred at a rate ≥ 1%, see Table 1.

Table 1: Treatment-Related Adverse Reactions at a Frequency ≥1%
Body System | PREMPRO 0.625 mg/2.5 mg continuous | PREMPRO 0.625 mg/5 mg continuous | PREMPHASE 0.625 mg/5 mg sequential
Adverse event | (n = 340) | (n = 338) | (n = 351)
Body As A Whole
Abdominal pain | 35 (10%) | 51 (15%) | 58 (17%)
Asthenia | 13 (4%) | 18 (5%) | 21 (6%)
Back pain | 19 (6%) | 16 (5%) | 23 (7%)
Chest pain | 5 (1%) | 4 (1%) | 4 (1%)
Flu syndrome | 1 (<1%) | 1 (<1%) | 4 (1%)
Generalized edema | 12 (4%) | 12 (4%) | 8 (2%)
Headache | 64 (19%) | 52 (15%) | 66 (19%)
Infection | 2 (<1%) | 4 (1)% | 0
Moniliasis | 4 (1%) | 3 (<1%) | 4 (1%)
Pain | 12 (4%) | 14 (4%) | 15 (4%)
Pelvic pain | 11 (3%) | 13 (4%) | 16 (5%)
Cardiovascular System
Hypertension | 7 (2%) | 7 (2%) | 6 (2%)
Migraine | 6 (2%) | 8 (2%) | 7 (2%)
Palpitation | 2 (<1%) | 3 (<1%) | 4 (1%)
Vasodilatation | 2 (<1%) | 7 (2%) | 2 (<1%)
Digestive System
Diarrhea | 4 (1%) | 3 (<1%) | 7 (2%)
Dyspepsia | 5 (1%) | 5 (1%) | 7 (2%)
Eructation | 0 | 2 (<1%) | 4 (1%)
Flatulence | 25 (7%) | 27 (8%) | 24 (7%)
Increased appetite | 1 (<1%) | 5 (1%) | 5 (1%)
Nausea | 26 (8%) | 19 (6%) | 26 (7%)
Metabolic and Nutritional
Edema | 5 (1%) | 6 (2%) | 3 (<1%)
Glucose tolerance decreased | 2 (<1%) | 5 (1%) | 4 (1%)
Peripheral edema | 11 (3%) | 10 (3%) | 11 (3%)
Weight gain | 9 (3%) | 10 (3%) | 11 (3%)
Musculoskeletal System
Arthralgia | 6 (2%) | 2 (<1%) | 7 (2%)
Leg cramps | 8 (2%) | 11 (3%) | 12 (3%)
Nervous System
Depression | 14 (4%) | 26 (8%) | 29 (8%)
Dizziness | 9 (3%) | 8 (2%) | 7 (2%)
Emotional lability | 5 (1%) | 5 (1%) | 6 (2%)
Hypertonia | 4 (1%) | 4 (1%) | 7 (2%)
Insomnia | 7 (2%) | 6 (2%) | 4 (1%)
Nervousness | 4 (1%) | 9 (3%) | 6 (2%)
Skin and Appendages
Acne | 1 (<1%) | 5 (1%) | 4 (1%)
Alopecia | 3 (<1%) | 4 (1%) | 0
Dry skin | 2 (<1%) | 3 (<1%) | 4 (1%)
Pruritus | 20 (6%) | 18 (5%) | 13 (4%)
Rash | 8 (2%) | 6 (2%) | 7 (2%)
Sweating | 2 (<1%) | 4 (1%) | 2 (<1%)
Urogenital System
Breast engorgement | 5 (1%) | 5 (1%) | 0
Breast enlargement | 14 (4%) | 14 (4%) | 14 (4%)
Breast neoplasm | 2 (<1%) | 2 (<1%) | 4 (1%)
Breast pain | 110 (32%) | 123 (36%) | 109 (31%)
Cervix disorder | 10 (3%) | 6 (2%) | 10 (3%)
Dysmenorrhea | 26 (8%) | 18 (5%) | 44 (13%)
Leukorrhea | 19 (6%) | 13 (4%) | 29 (8%)
Menstrual disorder | 7 (2%) | 1 (<1%) | 5 (1%)
Menorrhagia | 0 | 1 (<1%) | 5 (1%)
Metrorrhagia | 13 (4%) | 5 (1%) | 7 (1%)
Papanicolaou smear suspicious | 5 (1%) | 0 | 8 (2%)
Urinary incontinence | 4 (1%) | 2 (<1%) | 1 (<1%)
Uterine spasm | 7 (2%) | 4 (1%) | 7 (2%)
Vaginal hemorrhage | 5 (1%) | 3 (<1%) | 8 (2%)
Vaginal moniliasis | 5 (1%) | 6 (2%) | 7 (2%)
Vaginitis | 13 (4%) | 13 (4%) | 10 (3%)

In addition, phargyngitis and sinusitis were reported as two of the more frequent adverse events (>5%) in the PREMPRO clinical study. For pharyngitis, of the 121 events, six events were considered by the investigator causally related to study drug. For sinusitis, of the 73 events, one event was considered as casually related to study drug.

During the first year of a 2-year clinical trial with postmenopausal women between 40 and 65 years of age (88% Caucasian), 989 postmenopausal women received continuous regimens of PREMPRO, and 332 received placebo tablets. Table 2 summarizes adverse reactions that occurred at a rate ≥ 1% in at least 1 treatment group.

Table 2: All Treatment-Related Adverse Reactions at a Frequency of ≥1%
Body System Adverse event | PREMPRO 0.625/2.5 continuous (N=331) | PREMPRO 0.45/1.5 continuous (N=331) | PREMPRO 0.3/1.5 continuous (N=327) | PLACEBO daily (N=332)
Any adverse event | 214 (65) | 208 (63) | 188 (57) | 164 (49)
Body as a Whole
Abdominal pain | 38 (11) | 33 (10) | 24 (7) | 21 (6)
Asthenia | 11 (3) | 11 (3) | 12 (4) | 3 (1)
Back pain | 12 (4) | 12 (4) | 8 (2) | 4 (1)
Chest pain | 4 (1) | 2 (1) | 1 (0) | 2 (1)
Generalized edema | 7 (2) | 5 (2) | 6 (2) | 8 (2)
Headache | 45 (14) | 45 (14) | 57 (17) | 46 (14)
Moniliasis | 3 (1) | 6 (2) | 4 (1) | 1 (0)
Pain | 9 (3) | 10 (3) | 17 (5) | 14 (4)
Pelvic pain | 9 (3) | 7 (2) | 5 (2) | 4 (1)
Cardiovascular System
Hypertension | 2 (1) | 3 (1) | 1 (0) | 5 (2)
Migraine | 11 (3) | 8 (2) | 5 (2) | 3 (1)
Palpitation | 1 (0) | 1 (0) | 2 (1) | 4 (1)
Vasodilatation | 0 | 3 (1) | 1 (0) | 5 (2)
Digestive System
Constipation | 5 (2) | 7 (2) | 6 (2) | 3 (1)
Diarrhea | 5 (2) | 2 (1) | 6 (2) | 8 (2)
Dyspepsia | 10 (3) | 9 (3) | 6 (2) | 14 (4)
Flatulence | 16 (5) | 18 (5) | 13 (4) | 8 (2)
Increased appetite | 6 (2) | 2 (1) | 0 | 2 (1)
Nausea | 13 (4) | 13 (4) | 16 (5) | 16 (5)
Metabolic and nutritional
Peripheral edema | 7 (2) | 8 (2) | 4 (1) | 3 (1)
Weight gain | 9 (3) | 8 (2) | 6 (2) | 14 (4)
Musculoskeletal System
Arthralgia | 2 (1) | 3 (1) | 3 (1) | 5 (2)
Leg cramps | 13 (4) | 7 (2) | 10 (3) | 4 (1)
Nervous System
Anxiety | 5 (2) | 4 (1) | 1 (0) | 4 (1)
Depression | 23 (7) | 11 (3) | 11 (3) | 17 (5)
Dizziness | 3 (1) | 8 (2) | 6 (2) | 5 (2)
Emotional lability | 10 (3) | 10 (3) | 9 (3) | 8 (2)
Insomnia | 8 (2) | 7 (2) | 9 (3) | 14 (4)
Nervousness | 6 (2) | 3 (1) | 4 (1) | 6 (2)
Skin and Appendages
Acne | 7 (2) | 3 (1) | 0 | 3 (1)
Alopecia | 1 (0) | 6 (2) | 4 (1) | 2 (1)
Pruritus | 8 (2) | 10 (3) | 9 (3) | 3 (1)
Rash | 0 | 6 (2) | 4 (1) | 2 (1)
Skin discoloration | 5 (2) | 1 (0) | 3 (1) | 1 (0)
Sweating | 3 (1) | 1 (0) | 0 | 4 (1)
Urogenital System
Breast disorder | 7 (2) | 6 (2) | 5 (2) | 6 (2)
Breast enlargement | 18 (5) | 9 (3) | 5 (2) | 3 (1)
Breast neoplasm | 8 (2) | 7 (2) | 5 (2) | 7 (2)
Breast pain | 87 (26) | 66 (20) | 41 (13) | 26 (8)
Cervix disorder | 7 (2) | 2 (1) | 2 (1) | 0
Dysmenorrhea | 14 (4) | 18 (5) | 9 (3) | 2 (1)
Hematuria | 4 (1) | 3 (1) | 1 (0) | 2 (1)
Leukorrhea | 7 (2) | 14 (4) | 9 (3) | 6 (2)
Metrorrhagia | 7 (2) | 14 (4) | 4 (1) | 1 (0)
Urinary tract infection | 0 | 1 (0) | 1 (0) | 4 (1)
Uterine spasm | 13 (4) | 11 (3) | 7 (2) | 2 (1)
Vaginal dryness | 2 (1) | 1 (0) | 0 | 6 (2)
Vaginal hemorrhage | 18 (5) | 14 (4) | 7 (2) | 0
Vaginal moniliasis | 13 (4) | 11 (3) | 8 (2) | 5 (2)
Vaginitis | 6 (2) | 8 (2) | 7 (2) | 1 (0)

In addition, the following events were considered as related to the study drug with an incidence less than 1%, including accidental injury, infection, myalgia, cough increased, rhinitis, sinusitis, and upper respiratory infection.

6.2 Postmarketing Experience

The following adverse reactions have been identified during post-approval use of PREMPRO or PREMPHASE. Because these reactions are reported voluntarily from a population of uncertain size, it is not always possible to reliably estimate their frequency or establish a causal relationship to drug exposure.

Genitourinary System

Abnormal uterine bleeding, dysmenorrhea or pelvic pain, increase in size of uterine leiomyomata, vaginitis, vaginal candidiasis, amenorrhea, changes in cervical secretion, ovarian cancer, endometrial hyperplasia, endometrial cancer.

Breasts

Tenderness, enlargement, pain, nipple discharge, galactorrhea, fibrocystic breast changes, breast cancer.

Cardiovascular

Deep and superficial venous thrombosis, pulmonary embolism, superficial thrombophlebitis, myocardial infarction, stroke, increase in blood pressure.

Gastrointestinal

Nausea, vomiting, abdominal pain, bloating, cholestatic jaundice, increased incidence of gallbladder disease, pancreatitis, changes in appetite, ischemic colitis.

Skin

Chloasma or melasma that may persist when drug is discontinued, erythema multiforme, erythema nodosum, loss of scalp hair, hirsutism, pruritus, urticaria, rash, acne.

Eyes

Retinal vascular thrombosis, intolerance of contact lenses.

Central Nervous System

Headache, migraine, dizziness, mental depression, exacerbation of chorea, mood disturbances, anxiety, irritability, exacerbation of epilepsy, dementia, growth potentiation of benign meningioma.

Miscellaneous

Increase or decrease in weight, arthralgia, glucose intolerance, edema, changes in libido, exacerbation of asthma, increased triglycerides, hypersensitivity.

Additional postmarketing adverse reactions have been reported in patients receiving other forms of hormone therapy.

7 DRUG INTERACTIONS

Data from a single-dose drug-drug interaction study involving CE and MPA indicate that the pharmacokinetic disposition of both drugs is not altered when the drugs are coadministered. No other clinical drug-drug interaction studies have been conducted with CE plus MPA.

7.1 Metabolic Interactions

In vitro and in vivo studies have shown that estrogens are metabolized partially by cytochrome P450 3A4 (CYP3A4). Therefore, inducers or inhibitors of CYP3A4 may affect estrogen drug metabolism. Inducers of CYP3A4, such as St. John's wort (Hypericum perforatum) preparations, phenobarbital, carbamazepine, and rifampin, may reduce plasma concentrations of estrogens, possibly resulting in a decrease in therapeutic effects and/or changes in the uterine bleeding profile. Inhibitors of CYP3A4, such as erythromycin, clarithromycin, ketoconazole, itraconazole, ritonavir and grapefruit juice, may increase plasma concentrations of estrogens and may result in side effects.

Aminoglutethimide administered concomitantly with MPA may significantly depress the bioavailability of MPA.

8 USE IN SPECIFIC POPULATIONS

8.1 Pregnancy

Risk Summary

PREMPRO and PREMPHASE are not indicated for use during pregnancy.

There are no data with the use of PREMPRO and PREMPHASE in pregnant women; however, epidemiologic studies and meta-analyses have not found an increased risk of genital or nongenital birth defects (including cardiac anomalies and limb-reduction defects) following exposure to combined hormonal contraceptives (estrogen and progestins) before conception or during early pregnancy.

In the U.S. general population, the estimated background risk of major birth defects and miscarriage in clinically recognized pregnancies is 2% to 4% and 15% to 20%, respectively.

8.2 Lactation

Risk Summary

Estrogens and progestins and metabolites are present in human milk. These hormones can reduce milk production in breast-feeding women. This reduction can occur at any time but is less likely to occur once breast-feeding is well established. The developmental and health benefits of breast-feeding should be considered along with the mother’s clinical need for PREMPRO or PREMPHASE and any potential adverse effects on the breast-fed child from PREMPRO or PREMPHASE or from the underlying maternal condition.

8.4 Pediatric Use

PREMPRO and PREMPHASE are not indicated in children. Clinical studies have not been conducted in the pediatric population.

8.5 Geriatric Use

There have not been sufficient numbers of geriatric women involved in clinical studies utilizing PREMPRO or PREMPHASE to determine whether those over 65 years of age differ from younger subjects in their response to PREMPRO or PREMPHASE.

The Women's Health Initiative Study

In the WHI estrogen plus progestin substudy (daily CE [0.625 mg] plus MPA [2.5 mg] versus placebo), there was a higher relative risk of nonfatal stroke and invasive breast cancer in women greater than 65 years of age [see Clinical Studies (14.6)].

In the WHI estrogen-alone substudy (daily CE [0.625 mg]-alone versus placebo), there was a higher relative risk of stroke in women greater than 65 years of age [see Clinical Studies (14.6)].

The Women's Health Initiative Memory Study

In the WHIMS ancillary studies of postmenopausal women 65 to 79 years of age, there was an increased risk of developing probable dementia in women receiving estrogen plus progestin or estrogen-alone when compared to placebo [see Warnings and Precautions (5.3), and Clinical Studies (14.7)].

Since both ancillary studies were conducted in women 65 to 79 years of age, it is unknown whether these findings apply to younger postmenopausal women^8 [see Warnings and Precautions (5.3), and Clinical Studies (14.7)].

8.6 Renal Impairment

The effects of renal impairment on the pharmacokinetics of PREMPRO or PREMPHASE have not been studied.

8.7 Hepatic Impairment

The effects of hepatic impairment on the pharmacokinetics of PREMPRO or PREMPHASE have not been studied.

10 OVERDOSAGE

Overdosage of estrogen plus progestin may cause nausea, vomiting, breast tenderness, abdominal pain, drowsiness and fatigue, and withdrawal bleeding may occur in women. Treatment of overdose consists of discontinuation of PREMPRO or PREMPHASE therapy with institution of appropriate symptomatic care.

11 DESCRIPTION

Premarin (conjugated estrogens tablets, USP) for oral administration contains a mixture obtained exclusively from natural sources, occurring as the sodium salts of water-soluble estrogen sulfates blended to represent the average composition of material derived from pregnant mares' urine. It is a mixture of sodium estrone sulfate and sodium equilin sulfate. It contains as concomitant components, as sodium sulfate conjugates, 17 α-dihydroequilin, 17 α-estradiol and 17 β-dihydroequilin.

Medroxyprogesterone acetate is a derivative of progesterone. It is a white to off-white, odorless, crystalline powder, stable in air, melting between 200°C and 210°C. It is freely soluble in chloroform, soluble in acetone and in dioxane, sparingly soluble in alcohol and in methanol, slightly soluble in ether, and insoluble in water. The chemical name for MPA is pregn-4-ene-3, 20-dione, 17-(acetyloxy)-6-methyl-, (6α)-. Its molecular formula is C24H34O4, with a molecular weight of 386.53. Its structural formula is:

PREMPRO 0.3 mg/1.5 mg and 0.45 mg/1.5 mg tablets contain the following inactive ingredients: calcium phosphate tribasic, microcrystalline cellulose, carnauba wax, hypromellose, hydroxypropyl cellulose, sucrose, Eudragit NE 30D, lactose monohydrate, magnesium stearate, polyethylene glycol, titanium dioxide, yellow iron oxide, propylene glycol and black iron oxide.

PREMPRO 0.625 mg/2.5 mg tablets contain the following inactive ingredients: calcium phosphate tribasic, microcrystalline cellulose, carnauba wax, hypromellose, hydroxypropyl cellulose, sucrose, Eudragit NE 30D, lactose monohydrate, magnesium stearate, polyethylene glycol, propylene glycol, titanium dioxide, red iron oxide, yellow iron oxide, and black iron oxide.

PREMPRO 0.625 mg/5 mg tablets contain the following inactive ingredients: calcium phosphate tribasic, carnauba wax, Eudragit NE 30D, hydroxypropyl cellulose, hypromellose, lactose monohydrate, magnesium stearate, microcrystalline cellulose, polyethylene glycol, sucrose, titanium dioxide, triethyl citrate, FD&C Blue No. 2, black iron oxide, and propylene glycol.

PREMPHASE

Each maroon Premarin tablets for oral administration contain 0.625 mg of CE and the following inactive ingredients: calcium phosphate tribasic, carnauba wax, hydroxypropyl cellulose, microcrystalline cellulose, powdered cellulose, hypromellose, lactose monohydrate, magnesium stearate, polyethylene glycol, sucrose, titanium dioxide, propylene glycol, FD&C Blue No. 2, and FD&C Red No. 40. These tablets comply with USP Dissolution Test 5.

Each light-blue tablet for oral administration contains 0.625 mg of CE, 5 mg of medroxyprogesterone acetate, and the following inactive ingredients: calcium phosphate tribasic, carnauba wax, Eudragit NE 30D, hydroxypropyl cellulose, hypromellose, lactose monohydrate, magnesium stearate, microcrystalline cellulose, polyethylene glycol, sucrose, titanium dioxide, triethyl citrate, FD&C Blue No. 2, black iron oxide, and propylene glycol.

PREMPRO

Tablet Strength | Tablet Color Contains
0.3 mg/1.5 mg | Yellow iron oxide and black iron oxide
0.45 mg/1.5 mg | Yellow iron oxide and black iron oxide
0.625 mg/2.5 mg | Red iron oxide, yellow iron oxide, and black iron oxide
0.625 mg/5 mg | FD&C Blue No. 2 and black iron oxide

PREMPHASE

Tablet Strength | Tablet Color Contains
0.625 mg | FD&C Blue No. 2 and FD&C Red No. 40
0.625 mg/5 mg | FD&C Blue No. 2 and black iron oxide

12 CLINICAL PHARMACOLOGY

12.1 Mechanism of Action

Endogenous estrogens are largely responsible for the development and maintenance of the female reproductive system and secondary sexual characteristics. Although circulating estrogens exist in a dynamic equilibrium of metabolic interconversions, estradiol is the principal intracellular human estrogen and is substantially more potent than its metabolites, estrone and estriol, at the receptor level.

The primary source of estrogen in normally cycling adult women is the ovarian follicle, which secretes 70 to 500 mcg of estradiol daily, depending on the phase of the menstrual cycle. After menopause, most endogenous estrogen is produced by conversion of androstenedione, which is secreted by the adrenal cortex, to estrone in the peripheral tissues. Thus, estrone and the sulfate-conjugated form, estrone sulfate, are the most abundant circulating estrogens in postmenopausal women.

Estrogens act through binding to nuclear receptors in estrogen-responsive tissues. To date, two estrogen receptors have been identified. These vary in proportion from tissue to tissue.

Circulating estrogens modulate the pituitary secretion of the gonadotropins, luteinizing hormone (LH) and FSH, through a negative feedback mechanism. Estrogens act to reduce the elevated levels of these gonadotropins seen in postmenopausal women.

Parenterally administered medroxyprogesterone acetate (MPA) inhibits gonadotropin production, which in turn prevents follicular maturation and ovulation; although available data indicate that this does not occur when the usually recommended oral dosage is given as single daily doses. MPA may achieve its beneficial effect on the endometrium in part by decreasing nuclear estrogen receptors and suppression of epithelial DNA synthesis in endometrial tissue. Androgenic and anabolic effects of MPA have been noted, but the drug is apparently devoid of significant estrogenic activity.

12.2 Pharmacodynamics

Currently, there are no pharmacodynamic data known for PREMPRO or PREMPHASE tablets.

12.3 Pharmacokinetics

Absorption

PREMPRO and PREMPHASE contain a formulation of medroxyprogesterone acetate (MPA) that is immediately released and CE that are slowly released over several hours. Conjugated estrogens are water-soluble and are well-absorbed from the gastrointestinal tract after release from the drug formulation. MPA is well absorbed from the gastrointestinal tract. Table 3 and Table 4 summarize the mean pharmacokinetic parameters for select unconjugated and conjugated estrogens and medroxyprogesterone acetate following administration of PREMPRO to healthy, postmenopausal women.

Table 3: Pharmacokinetic Parameters for Unconjugated and Conjugated Estrogens (CE) and Medroxyprogesterone Acetate (MPA)
DRUG | 2 × 0.625 mg CE/2.5 mg MPA Combination Tablets (n = 54) |  |  |  | 2 × 0.625 mg CE/5 mg MPA Combination Tablets (n = 51)
PK Parameter Arithmetic Mean (%CV) | Cmax (pg/mL) | tmax (h) | t1/2 (h) | AUC (pg∙h/mL) | Cmax (pg/mL) | tmax (h) | t1/2 (h) | AUC (pg∙h/mL)
Unconjugated Estrogens
Estrone | 175 (23) | 7.6 (24) | 31.6 (23) | 5358 (34) | 124 (43) | 10 (35) | 62.2 (137) | 6303 (40)
BA* -Estrone | 159 (26) | 7.6 (24) | 16.9 (34) | 3313 (40) | 104 (49) | 10 (35) | 26.0 (100) | 3136 (51)
Equilin | 71 (31) | 5.8 (34) | 9.9 (35) | 951 (43) | 54 (43) | 8.9 (34) | 15.5 (53) | 1179 (56)
PK Parameter Arithmetic Mean (%CV) | Cmax (ng/mL) | tmax (h) | t1/2 (h) | AUC (ng∙h/mL) | Cmax (ng/mL) | tmax (h) | t1/2 (h) | AUC (ng∙h/mL)
Conjugated Estrogens
Total Estrone | 6.6 (38) | 6.1 (28) | 20.7 (34) | 116 (59) | 6.3 (48) | 9.1 (29) | 23.6 (36) | 151 (42)
BA* -Total Estrone | 6.4 (39) | 6.1 (28) | 15.4 (34) | 100 (57) | 6.2 (48) | 9.1 (29) | 20.6 (35) | 139 (40)
Total Equilin | 5.1 (45) | 4.6 (35) | 11.4 (25) | 50 (70) | 4.2 (52) | 7.0 (36) | 17.2 (131) | 72 (50)
PK Parameter Arithmetic Mean (%CV) | Cmax (ng/mL) | tmax (h) | t1/2 (h) | AUC (ng∙h/mL) | Cmax (ng/mL) | tmax (h) | t1/2 (h) | AUC (ng∙h/mL)
Medroxyprogesterone Acetate
MPA | 1.5 (40) | 2.8 (54) | 37.6 (30) | 37 (30) | 4.8 (31) | 2.4 (50) | 46.3 (39) | 102 (28)
BA* = Baseline adjusted
Cmax = peak plasma concentration
tmax = time peak concentration occurs
t1/2 = apparent terminal-phase disposition half-life (0.693/λz)
AUC = total area under the concentration-time curve

TABLE 4. Pharmacokinetic Parameters for Unconjugated and Conjugated Estrogens (CE) and Medroxyprogesterone Acetate (MPA)
DRUG | 4 × 0.45 mg CE/1.5 mg MPA Combination (n = 65)
PK Parameter Arithmetic Mean (%CV) | Cmax (pg/mL) | tmax (h) | t1/2 (h) | AUC (pg∙h/mL)
Unconjugated Estrogens
Estrone | 149 (35) | 8.9 (35) | 37.5 (35) | 6641 (39)
BA* -Estrone | 130 (40) | 8.9 (35) | 21.2 (35) | 3799 (47)
Equilin | 83 (38) | 8.3 (48) | 15.9 (44) | 1889 (40)
PK Parameter Arithmetic Mean (%CV) | Cmax (ng/mL) | tmax (h) | t1/2 (h) | AUC (ng∙h/mL)
Conjugated Estrogens
Total Estrone | 5.4 (49) | 7.9 (48) | 22.4 (53) | 119 (48)
BA* -Total Estrone | 5.2 (48) | 7.9 (48) | 15.1 (29) | 100 (47)
Total Equilin | 4.3 (42) | 6.5 (45) | 11.6 (31) | 74 (48)
PK Parameter Arithmetic Mean (%CV) | Cmax (ng/mL) | tmax (h) | t1/2 (h) | AUC (ng∙h/mL)
Medroxyprogesterone Acetate
MPA | 0.7 (66) | 2.0 (52) | 26.2 (35) | 5.0 (61)
BA* = Baseline adjusted
Cmax = peak plasma concentration
tmax = time peak concentration occurs
t1/2 = apparent terminal-phase disposition half-life (0.693/λz)
AUC = total area under the concentration-time curve

Food-Effect: Single dose studies in healthy, postmenopausal women were conducted to investigate any potential drug interaction when PREMPRO or PREMPHASE is administered with a high-fat breakfast. Administration with food decreased the Cmax of total estrone by 18 to 34% and increased total equilin Cmax by 38% compared to the fasting state, with no other effect on the rate or extent of absorption of other conjugated or unconjugated estrogens. Administration with food approximately doubles MPA Cmax and increases MPA AUC by approximately 20 to 30%.

Dose Proportionality: The Cmax and AUC values for MPA observed in two separate pharmacokinetic studies conducted with 2 PREMPRO 0.625 mg/2.5 mg or 2 PREMPRO or PREMPHASE 0.625 mg/5 mg tablets exhibited nonlinear dose proportionality; doubling the MPA dose from 2 × 2.5 to 2 × 5 mg increased the mean Cmax and AUC by 3.2- and 2.8-fold, respectively.

The dose proportionality of estrogens and medroxyprogesterone acetate was assessed by combining pharmacokinetic data across another two studies totaling 61 healthy, postmenopausal women. Single CE doses of 2 × 0.3 mg, 2 × 0.45 mg, or 2 × 0.625 mg were administered either alone or in combination with medroxyprogesterone acetate doses of 2 × 1.5 mg or 2 × 2.5 mg. Most of the estrogen components demonstrated dose proportionality; however, several estrogen components did not. Medroxyprogesterone acetate pharmacokinetic parameters increased in a dose-proportional manner.

Distribution

The distribution of exogenous estrogens is similar to that of endogenous estrogens. Estrogens are widely distributed in the body and are generally found in higher concentrations in the sex hormone target organs. Estrogens circulate in the blood largely bound to SHBG and albumin. MPA is approximately 90% bound to plasma proteins, but does not bind to SHBG.

Metabolism

Exogenous estrogens are metabolized in the same manner as endogenous estrogens. Circulating estrogens exist in a dynamic equilibrium of metabolic interconversions. These transformations take place mainly in the liver. Estradiol is converted reversibly to estrone, and both can be converted to estriol, which is a major urinary metabolite. Estrogens also undergo enterohepatic recirculation via sulfate and glucuronide conjugation in the liver, biliary secretion of conjugates into the intestine, and hydrolysis in the intestine followed by reabsorption. In postmenopausal women, a significant proportion of the circulating estrogens exist as sulfate conjugates, especially estrone sulfate, which serves as a circulating reservoir for the formation of more active estrogens. Metabolism and elimination of MPA occur primarily in the liver via hydroxylation, with subsequent conjugation and elimination in the urine.

Excretion

Estradiol, estrone, and estriol are excreted in the urine along with glucuronide and sulfate conjugates. Most metabolites of MPA are excreted as glucuronide conjugates, with only minor amounts excreted as sulfates.

Use in Specific Populations

No pharmacokinetic studies were conducted in specific populations, including patients with renal or hepatic impairment.

13 NONCLINICAL TOXICOLOGY

13.1 Carcinogenesis, Mutagenesis, Impairment of Fertility

Long-term continuous administration of natural and synthetic estrogens in certain animal species increases the frequency of carcinomas of the breasts, uterus, cervix, vagina, testis, and liver [see Warnings and Precautions (5.2)].

MPA was not mutagenic in a battery of in vitro or in vivo genetic toxicity assays [see Warnings and Precautions (5.7)].

14 CLINICAL STUDIES

14.1 Effects on Vasomotor Symptoms

In the first year of the Health and Osteoporosis, Progestin and Estrogen (HOPE) Study, a total of 2,805 postmenopausal women (average age 53.3 ± 4.9 years) were randomly assigned to one of eight treatment groups of either placebo or CE, with or without MPA. Efficacy for vasomotor symptoms was assessed during the first 12 weeks of treatment in a subset of symptomatic women (n = 241) who had at least seven moderate to severe hot flushes daily, or at least 50 moderate to severe hot flushes during the week before randomization. With PREMPRO 0.625 mg/2.5 mg, 0.45 mg/1.5 mg, and 0.3 mg/1.5 mg, the relief of both the frequency and severity of moderate to severe vasomotor symptoms was shown to be statistically improved compared to placebo at weeks 4 and 12. Table 5 shows the adjusted mean number of hot flushes in the PREMPRO 0.625 mg/2.5 mg, 0.45 mg/1.5 mg, 0.3 mg/1.5 mg, and placebo groups during the initial 12-week period.

Table 5: Summary Tabulation of the Number of Hot Flushes Per Day – Mean Values and Comparisons Between the Active Treatment Groups and the Placebo Group – Patients with At Least 7 Moderate to Severe Flushes Per Day or At Least 50 Per Week at Baseline, Last Observation Carries Forward (LOCF)
Treatment [Identified by dosage (mg) of Premarin/MPA or placebo.] (No. of Patients) | -------------------No. of Hot Flushes/Day-----------------
Time Period (week) | Baseline Mean ± SD | Observed Mean ± SD | Mean Change ± SD | p-Values vs. Placebo [There were no statistically significant differences between the 0.625 mg/2.5 mg, 0.45 mg/1.5 mg, and 0.3 mg/1.5 mg groups at any time period.]
0.625 mg/2.5 mg (n = 34)
4 | 11.98 ± 3.54 | 3.19 ± 3.74 | -8.78 ± 4.72 | <0.001
12 | 11.98 ± 3.54 | 1.16 ± 2.22 | -10.82 ± 4.61 | <0.001
0.45 mg/1.5 mg (n = 29)
4 | 12.61 ± 4.29 | 3.64 ± 3.61 | -8.98 ± 4.74 | <0.001
12 | 12.61 ± 4.29 | 1.69 ± 3.36 | -10.92 ± 4.63 | <0.001
0.3 mg/1.5 mg (n = 33)
4 | 11.30 ± 3.13 | 3.70 ± 3.29 | -7.60 ± 4.71 | <0.001
12 | 11.30 ± 3.13 | 1.31 ± 2.82 | -10.00 ± 4.60 | <0.001
Placebo (n = 28)
4 | 11.69 ± 3.87 | 7.89 ± 5.28 | -3.80 ± 4.71 | -
12 | 11.69 ± 3.87 | 5.71 ± 5.22 | -5.98 ± 4.60 | -

14.2 Effects on Vulvar and Vaginal Atrophy

Results of vaginal maturation indexes at cycles 6 and 13 showed that the differences from placebo were statistically significant (p < 0.001) for all treatment groups.

14.3 Effects on the Endometrium

In a 1-year clinical trial of 1,376 women (average age 54 ± 4.6 years) randomized to PREMPRO 0.625 mg/2.5 mg (n = 340), PREMPRO 0.625 mg/5 mg (n = 338), PREMPHASE 0.625 mg/5 mg (n = 351), or Premarin 0.625 mg alone (n = 347), results of evaluable biopsies at 12 months (n = 279, 274, 277, and 283, respectively) showed a reduced risk of endometrial hyperplasia in the two PREMPRO treatment groups (less than 1%) and in the PREMPHASE treatment group (less than 1%; 1% when focal hyperplasia was included) compared to the Premarin group (8%; 20% when focal hyperplasia was included), see Table 6.

Table 6: Incidence of Endometrial Hyperplasia After One Year of Treatment
 | --------------------------Groups-------------------------
 | PREMPRO | PREMPRO | PREMPHASE | Premarin
 | 0.625 mg/2.5 mg | 0.625 mg/5 mg | 0.625 mg/5 mg | 0.625 mg
Total number of patients | 340 | 338 | 351 | 347
Number of patients with evaluable biopsies | 279 | 274 | 277 | 283
No. (%) of patients with biopsies:
• All focal and non-focal hyperplasia | 2 (<1) [Significant (p < 0.001) in comparison with Premarin (0.625 mg) alone.] | 0 (0) | 3 (1) | 57 (20)
• Excluding focal cystic hyperplasia | 2 (<1) | 0 (0) | 1 (<1) | 25 (8)

In the first year of the Health and Osteoporosis, Progestin and Estrogen (HOPE) Study, 2,001 women (average age 53.3 ± 4.9 years), of whom 88% were Caucasian, were treated with either Premarin 0.625 mg alone (n = 348), Premarin 0.45 mg alone (n = 338), Premarin 0.3 mg alone (n = 326) or PREMPRO 0.625 mg/2.5 mg (n = 331), PREMPRO 0.45 mg/1.5 mg (n = 331) or PREMPRO 0.3 mg/1.5 mg (n = 327). Results of evaluable endometrial biopsies at 12 months showed a reduced risk of endometrial hyperplasia or cancer in the PREMPRO treatment groups compared with the corresponding Premarin alone treatment groups, except for the PREMPRO 0.3 mg/1.5 mg and Premarin 0.3 mg alone groups, in each of which there was only 1 case, see Table 7.

No endometrial hyperplasia or cancer was noted in those patients treated with the continuous combined regimens who continued for a second year in the osteoporosis and metabolic substudy of the HOPE study, see Table 8.

Table 7: Incidence of Endometrial Hyperplasia/Cancer [All cases of hyperplasia/cancer were endometrial hyperplasia, except for 1 patient in the Premarin 0.3 mg group diagnosed with endometrial cancer based on endometrial biopsy and 1 patient in the Premarin/MPA 0.45 mg/1.5 mg group diagnosed with endometrial cancer based on endometrial biopsy.] After One Year of Treatment [Two (2) primary pathologists evaluated each endometrial biopsy. Where there was lack of agreement on the presence or absence of hyperplasia/cancer between the two, a third pathologist adjudicated (consensus).]
 | -----------------------------------Groups---------------------------------
Patient | Prempro 0.625 mg/2.5 mg | Premarin 0.625 mg | Prempro 0.45 mg/1.5 mg | Premarin 0.45 mg | Prempro 0.3 mg/1.5 mg | Premarin 0.3 mg
Total number of patients | 331 | 348 | 331 | 338 | 327 | 326
Number of patients with evaluable biopsies | 278 | 249 | 272 | 279 | 271 | 269
No. (%) of patients with biopsies:
• Hyperplasia/cancer (consensus [For an endometrial biopsy to be counted as consensus endometrial hyperplasia or cancer, at least 2 pathologists had to agree on the diagnosis.]) | 0 (0) [Significant (p < 0.05) in comparison with corresponding dose of Premarin alone.] | 20 (8) | 1 (<1), | 9 (3) | 1 (<1) [Non-significant in comparison with corresponding dose of Premarin alone.] | 1 (<1)

Table 8: Osteoporosis and Metabolic Substudy, Incidence of Endometrial Hyperplasia/Cancer [All cases of hyperplasia/cancer were endometrial hyperplasia in patients who continued for a second year in the osteoporosis and metabolic substudy of the HOPE study.] After Two Years of Treatment [Two (2) primary pathologists evaluated each endometrial biopsy. Where there was lack of agreement on the presence or absence of hyperplasia/cancer between the two, a third pathologist adjudicated (consensus).]
 | -------------------------------Groups------------------------------
Patient | Prempro 0.625 mg/2.5 mg | Premarin 0.625 mg | Prempro 0.45 mg/1.5 mg | Premarin 0.45 mg | Prempro 0.3 mg/1.5 mg | Premarin 0.3 mg
Total number of patients | 75 | 65 | 75 | 74 | 79 | 73
Number of patients with evaluable biopsies | 62 | 55 | 69 | 67 | 75 | 63
No. (%) of patients with biopsies:
• Hyperplasia/cancer (consensus [For an endometrial biopsy to be counted as consensus endometrial hyperplasia or cancer, at least 2 pathologists had to agree on the diagnosis.]) | 0 (0) [Significant (p < 0.05) in comparison with corresponding dose of Premarin alone.] | 15 (27) | 0 (0) | 10 (15) | 0 (0) | 2 (3)

14.4 Effects on Uterine Bleeding or Spotting

The effects of PREMPRO on uterine bleeding or spotting, as recorded on daily diary cards, were evaluated in 2 clinical trials. Results are shown in Figures 1 and 2.

Figure 1. Patients With Cumulative Amenorrhea Over Time Percentages of Women With No Bleeding Or Spotting at a Given Cycle Through Cycle 13 Intent-To-Treat Population, LOCF

Note: The percentage of patients who were amenorrheic in a given cycle and through cycle 13 is shown. If data were missing, the bleeding value from the last reported day was carried forward (LOCF).

Figure 2. Patients With Cumulative Amenorrhea Over Time Percentages of Women With No Bleeding or Spotting at a Given Cycle Through Cycle 13 Intent-To-Treat Population, LOCF

Note: The percentage of patients who were amenorrheic in a given cycle and through cycle 13 is shown. If data were missing, the bleeding value from the last reported day was carried forward (LOCF).

14.5 Effects on Bone Mineral Density

Health and Osteoporosis, Progestin and Estrogen (HOPE) Study

The HOPE study was a double-blind, randomized, placebo/active-drug-controlled, multicenter study of healthy postmenopausal women with an intact uterus. Subjects (mean age 53.3 ± 4.9 years) were 2.3 ± 0.9 years on average since menopause and took one 600 mg tablet of elemental calcium (Caltrate™) daily. Subjects were not given Vitamin D supplements. They were treated with PREMPRO 0.625 mg/2.5 mg, 0.45 mg/1.5 mg or 0.3 mg/1.5 mg, comparable doses of Premarin alone, or placebo. Prevention of bone loss was assessed by measurement of bone mineral density (BMD), primarily at the anteroposterior lumbar spine (L2 to L4). Secondarily, BMD measurements of the total body, femoral neck, and trochanter were also analyzed. Serum osteocalcin, urinary calcium, and N-telopeptide were used as bone turnover markers (BTM) at cycles 6, 13, 19, and 26.

Intent-to-treat subjects

All active treatment groups showed significant differences from placebo in each of the four BMD endpoints. These significant differences were seen at cycles 6, 13, 19, and 26.

The percent changes from baseline to final evaluation are shown in Table 9.

Table 9: Percent Change in Bone Mineral Density: Comparison Between Active and Placebo Groups in the Intent-To-Treat Population, LOCF
Region Evaluated Treatment Group [Identified by dosage (mg/mg) of Premarin/MPA or placebo.] | No. of Subjects | Baseline (g/cm^2) Mean ± SD | Change from Baseline (%) Adjusted Mean ± SE | p-Value vs. Placebo
L2 to L4 BMD
0.625/2.5 | 81 | 1.14 ± 0.16 | 3.28 ± 0.37 | <0.001
0.45/1.5 | 89 | 1.16 ± 0.14 | 2.18 ± 0.35 | <0.001
0.3/1.5 | 90 | 1.14 ± 0.15 | 1.71 ± 0.35 | <0.001
Placebo | 85 | 1.14 ± 0.14 | -2.45 ± 0.36
Total body BMD
0.625/2.5 | 81 | 1.14 ± 0.08 | 0.87 ± 0.17 | <0.001
0.45/1.5 | 89 | 1.14 ± 0.07 | 0.59 ± 0.17 | <0.001
0.3/1.5 | 91 | 1.13 ± 0.08 | 0.60 ± 0.16 | <0.001
Placebo | 85 | 1.13 ± 0.08 | -1.50 ± 0.17
Femoral neck BMD
0.625/2.5 | 81 | 0.89 ± 0.14 | 1.62 ± 0.46 | <0.001
0.45/1.5 | 89 | 0.89 ± 0.12 | 1.48 ± 0.44 | <0.001
0.3/1.5 | 91 | 0.86 ± 0.11 | 1.31 ± 0.43 | <0.001
Placebo | 85 | 0.88 ± 0.14 | -1.72 ± 0.45
Femoral trochanter BMD
0.625/2.5 | 81 | 0.77 ± 0.14 | 3.35 ± 0.59 | 0.002
0.45/1.5 | 89 | 0.76 ± 0.12 | 2.84 ± 0.57 | 0.011
0.3/1.5 | 91 | 0.76 ± 0.12 | 3.93 ± 0.56 | <0.001
Placebo | 85 | 0.75 ± 0.12 | 0.81 ± 0.58

Figure 3 shows the cumulative percentage of subjects with percent changes from baseline in spine BMD equal to or greater than the percent change shown on the x-axis.

Figure 3. Cumulative Percent of Subjects With Changes from Baseline in Spine BMD of Given Magnitude or Greater in PREMARIN/MPA and Placebo Groups

The mean percent changes from baseline in L2 to L4 BMD for women who completed the bone density study are shown with standard error bars by treatment group in Figure 4. Significant differences between each of the PREMPRO dosage groups and placebo were found at cycles 6, 13, 19, and 26.

Figure 4. Adjusted Mean (SE) Percent Change from Baseline at Each Cycle in Spine BMD: Subjects Completing in PREMARIN/MPA Groups and Placebo

The bone turnover markers, serum osteocalcin and urinary N-telopeptide, significantly decreased (p < 0.001) in all active-treatment groups at cycles 6, 13, 19, and 26 compared with the placebo group. Larger mean decreases from baseline were seen with the active groups than with the placebo group. Significant differences from placebo were seen less frequently in urine calcium; only with PREMPRO 0.625 mg/2.5 mg and 0.45 mg/1.5 mg were there significantly larger mean decreases than with placebo at 3 or more of the 4 time points.

14.6 Women's Health Initiative Studies

The WHI enrolled approximately 27,000 predominantly healthy postmenopausal women in two substudies to assess the risks and benefits of daily oral CE (0.625 mg)-alone or in combination with MPA (2.5 mg) compared to placebo in the prevention of certain chronic diseases. The primary endpoint was the incidence of CHD (defined as nonfatal MI, silent MI and CHD death), with invasive breast cancer as the primary adverse outcome. A "global index" included the earliest occurrence of CHD, invasive breast cancer, stroke, PE, endometrial cancer (only in the CE plus MPA substudy), colorectal cancer, hip fracture, or death due to other causes. These substudies did not evaluate the effects of CE plus MPA or CE-alone on menopausal symptoms.

WHI Estrogen Plus Progestin Substudy

The WHI estrogen plus progestin substudy was stopped early. According to the predefined stopping rule, after an average follow-up of 5.6 years of treatment, the increased risk of invasive breast cancer and cardiovascular events exceeded the specified benefits included in the "global index." The absolute excess risk of events included in the "global index" was 19 per 10,000 women-years.

For those outcomes included in the WHI "global index" that reached statistical significance after 5.6 years of follow-up, the absolute excess risks per 10,000 women-years in the group treated with CE plus MPA were 7 more CHD events, 8 more strokes, 10 more PEs, and 8 more invasive breast cancers, while the absolute risk reductions per 10,000 women-years were 6 fewer colorectal cancers and 5 fewer hip fractures.

Results of the CE plus MPA substudy, which included 16,608 women (average 63 years of age, range 50 to 79; 83.9% White, 6.8% Black, 5.4% Hispanic, 3.9% Other) are presented in Table 10. These results reflect centrally adjudicated data after an average follow-up of 5.6 years.

TABLE 10: Relative and Absolute Risk Seen in the Estrogen Plus Progestin Substudy of WHI at an Average of 5.6 Years [Adapted from numerous WHI publications. WHI publications can be viewed at www.nhlbi.nih.gov/whi.] , [Results are based on centrally adjudicated data.]
 | Relative Risk CE/MPA vs. Placebo (95% nCI [Nominal confidence intervals unadjusted for multiple looks and multiple comparisons.]) | CE/MPA n = 8,506 | Placebo n = 8,102
Event |  | Absolute Risk per 10,000 Women-Years
CHD events | 1.23 (0.99–1.53) | 41 | 34
Non-fatal MI | 1.28 (1.00–1.63) | 31 | 25
CHD death | 1.10 (0.70–1.75) | 8 | 8
All Strokes | 1.31 (1.03–1.68) | 33 | 25
Ischemic stroke | 1.44 (1.09–1.90) | 26 | 18
Deep vein thrombosis [Not included in "global index."] | 1.95 (1.43–2.67) | 26 | 13
Pulmonary embolism | 2.13 (1.45–3.11) | 18 | 8
Invasive breast cancer [Includes metastatic and non-metastatic breast cancer, with the exception of in situ breast cancer.] | 1.24 (1.01–1.54) | 41 | 33
Colorectal cancer | 0.61 (0.42–0.87) | 10 | 16
Endometrial cancer | 0.81 (0.48–1.36) | 6 | 7
Cervical cancer | 1.44 (0.47–4.42) | 2 | 1
Hip fracture | 0.67 (0.47–0.96) | 11 | 16
Vertebral fractures | 0.65 (0.46–0.92) | 11 | 17
Lower arm/wrist fractures | 0.71 (0.59–0.85) | 44 | 62
Total fractures | 0.76 (0.69–0.83) | 152 | 199
Overall Mortality [All deaths, except from breast or colorectal cancer, definite or probable CHD, PE or cerebrovascular disease.] | 1.00 (0.83–1.19) | 52 | 52
Global Index [A subset of the events was combined in a "global index" defined as the earliest occurrence of CHD events, invasive breast cancer, stroke, pulmonary embolism, colorectal cancer, hip fracture, or death due to other causes.] | 1.13 (1.02–1.25) | 184 | 165

Timing of the initiation of estrogen plus progestin therapy relative to the start of menopause may affect the overall risk benefit profile. The WHI estrogen plus progestin substudy stratified by age showed in women 50 to 59 years of age, a non-significant trend toward reduced risk for overall mortality [hazard ratio (HR) 0.69 (95% CI, 0.44–1.07)].

WHI Estrogen-Alone Substudy

The WHI estrogen-alone substudy was stopped early because an increased risk of stroke was observed, and it was deemed that no further information would be obtained regarding the risks and benefits of estrogen-alone in predetermined primary endpoints.

Results of the estrogen-alone substudy, which included 10,739 women (average 63 years of age, range 50 to 79; 75.3% White, 15.1% Black, 6.1% Hispanic, 3.6% Other) after an average follow-up of 7.1 years, are presented in Table 11.

Table 11: Relative and Absolute Risk Seen in the Estrogen-Alone Substudy of WHI [Adapted from numerous WHI publications. WHI publications can be viewed at www.nhlbi.nih.gov/whi.]
 | Relative Risk CE vs. Placebo (95% nCI [Nominal confidence intervals unadjusted for multiple looks and multiple comparisons.]) | CE n = 5,310 | Placebo n = 5,429
Event |  | Absolute Risk per 10,000 Women-Years
CHD events [Results are based on centrally adjudicated data for an average follow-up of 7.1 years.] | 0.95 (0.78–1.16) | 54 | 57
Non-fatal MI | 0.91 (0.73–1.14) | 40 | 43
CHD death | 1.01 (0.71–1.43) | 16 | 16
All Strokes | 1.33 (1.05–1.68) | 45 | 33
Ischemic stroke | 1.55 (1.19–2.01) | 38 | 25
Deep vein thrombosis, [Not included in "global index."] | 1.47 (1.06–2.06) | 23 | 15
Pulmonary embolism | 1.37 (0.90–2.07) | 14 | 10
Invasive breast cancer | 0.80 (0.62–1.04) | 28 | 34
Colorectal cancer [Results are based on an average follow-up of 6.8 years.] | 1.08 (0.75–1.55) | 17 | 16
Hip fracture | 0.65 (0.45–0.94) | 12 | 19
Vertebral fractures, | 0.64 (0.44–0.93) | 11 | 18
Lower arm/wrist fractures, | 0.58 (0.47–0.72) | 35 | 59
Total fractures, | 0.71 (0.64–0.80) | 144 | 197
Death due to other causes, [All deaths, except from breast or colorectal cancer, definite or probable CHD, PE or cerebrovascular disease.] | 1.08 (0.88–1.32) | 53 | 50
Overall mortality, | 1.04 (0.88–1.22) | 79 | 75
Global Index [A subset of the events was combined in a "global index" defined as the earliest occurrence of CHD events, invasive breast cancer, stroke, pulmonary embolism, colorectal cancer, hip fracture, or death due to other causes.] | 1.02 (0.92–1.13) | 206 | 201

For those outcomes included in the WHI "global index" that reached statistical significance, the absolute excess risk per 10,000 women-years in the group treated with CE-alone was 12 more strokes while the absolute risk reduction per 10,000 women-years was 7 fewer hip fractures.^9 The absolute excess risk of events included in the "global index" was a non-significant 5 events per 10,000 women-years. There was no difference between the groups in terms of all-cause mortality.

No overall difference for primary CHD events (nonfatal MI, silent MI and CHD death) and invasive breast cancer incidence in women receiving CE-alone compared with placebo was reported in final centrally adjudicated results from the estrogen-alone substudy, after an average follow up of 7.1 years.

Centrally adjudicated results for stroke events from the estrogen-alone substudy, after an average follow-up of 7.1 years, reported no significant difference in distribution of stroke subtype or severity, including fatal strokes, in women receiving CE-alone compared to placebo. Estrogen-alone increased the risk for ischemic stroke, and this excess risk was present in all subgroups of women examined.^10

Timing of the initiation of estrogen-alone therapy relative to the start of menopause may affect the overall risk benefit profile. The WHI estrogen-alone substudy, stratified by age, showed in women 50 to 59 years of age a non-significant trend toward reduced risk for CHD [HR 0.63 (95% CI, 0.36–1.09)] and overall mortality [HR 0.71 (95% CI, 0.46–1.11)].

14.7 Women's Health Initiative Memory Study

The WHIMS estrogen plus progestin ancillary study of WHI enrolled 4,532 predominantly healthy postmenopausal women 65 years of age and older (47% were 65 to 69 years of age; 35% were 70 to 74 years of age; and 18% were 75 years of age and older) to evaluate the effects of daily CE (0.625 mg) plus MPA (2.5 mg) on the incidence of probable dementia (primary outcome) compared to placebo.

After an average follow-up of 4 years, the relative risk of probable dementia for CE plus MPA versus placebo was 2.05 (95% CI, 1.21–3.48). The absolute risk of probable dementia for CE plus MPA versus placebo was 45 versus 22 cases per 10,000 women-years. Probable dementia as defined in this study included Alzheimer's disease (AD), vascular dementia (VaD) and mixed types (having features of both AD and VaD). The most common classification of probable dementia in the treatment group and the placebo group was AD. Since the ancillary study was conducted in women 65 to 79 years of age, it is unknown whether these findings apply to younger postmenopausal women [see Warnings and Precautions (5.3), and Use in Specific Populations (8.5)].

The WHIMS estrogen-alone ancillary study of WHI enrolled 2,947 predominantly healthy hysterectomized postmenopausal women 65 to 79 years of age and older (45% were 65 to 69 years of age; 36% were 70 to 74 years of age; 19% were 75 years of age and older) to evaluate the effects of daily CE (0.625 mg)-alone on the incidence of probable dementia (primary outcome) compared to placebo.

After an average follow-up of 5.2 years, the relative risk of probable dementia for CE-alone versus placebo was 1.49 (95% CI, 0.83–2.66). The absolute risk of probable dementia for CE‑alone versus placebo was 37 versus 25 cases per 10,000 women-years. Probable dementia as defined in this study included AD, VaD and mixed types (having features of both AD and VaD). The most common classification of probable dementia in the treatment group and the placebo group was AD. Since the ancillary study was conducted in women 65 to 79 years of age, it is unknown whether these findings apply to younger postmenopausal women [see Warnings and Precautions (5.3), and Use in Specific Populations (8.5)].

When data from the two populations were pooled as planned in the WHIMS protocol, the reported overall relative risk for probable dementia was 1.76 (95% CI, 1.19–2.60). Differences between groups became apparent in the first year of treatment. It is unknown whether these findings apply to younger postmenopausal women [see Warnings and Precautions (5.3), and Use in Specific Populations (8.5)].

15 REFERENCES

1. Rossouw JE, et al. Postmenopausal Hormone Therapy and Risk of Cardiovascular Disease by Age and Years Since Menopause. JAMA. 2007;297:1465–1477.
2. Hsia J, et al. Conjugated Equine Estrogens and Coronary Heart Disease. Arch Int Med. 2006;166:357–365.
3. Cushman M, et al. Estrogen Plus Progestin and Risk of Venous Thrombosis. JAMA. 2004;292:1573–1580.
4. Curb JD, et al. Venous Thrombosis and Conjugated Equine Estrogen in Women Without a Uterus. Arch Int Med. 2006;166:772–780.
5. Stefanick ML, et al. Effects of Conjugated Equine Estrogens on Breast Cancer and Mammography Screening in Postmenopausal Women With Hysterectomy. JAMA. 2006;295:1647-1657.
6. Chlebowski RT, et al. Influence of Estrogen Plus Progestin on Breast Cancer and Mammography in Healthy Postmenopausal Women. JAMA. 2003;289:3234–3253.
7. Anderson GL, et al. Effects of Estrogen Plus Progestin on Gynecologic Cancers and Associated Diagnostic Procedures. JAMA. 2003;290:1739–1748.
8. Shumaker SA, et al. Conjugated Equine Estrogens and Incidence of Probable Dementia and Mild Cognitive Impairment in Postmenopausal Women. JAMA. 2004;291:2947–2958.
9. Jackson RD, et al. Effects of Conjugated Equine Estrogen on Risk of Fractures and BMD in Postmenopausal Women With Hysterectomy: Results From the Women's Health Initiative Randomized Trial. J Bone Miner Res. 2006;21:817–828.
10. Hendrix SL, et al. Effects of Conjugated Equine Estrogen on Stroke in the Women's Health Initiative. Circulation. 2006;113:2425–2434.

16 HOW SUPPLIED/STORAGE AND HANDLING

16.1 How Supplied

PREMPRO therapy consists of a single tablet to be taken once daily.

PREMPRO 0.3 mg/1.5 mg

NDC 0046-1105-11, carton includes 1 blister card containing 28 oval, cream tablets.

PREMPRO 0.45 mg/1.5 mg

NDC 0046-1106-11, carton includes 1 blister card containing 28 oval, gold tablets.

PREMPRO 0.625 mg/2.5 mg

NDC 0046-1107-11, carton includes 1 blister card containing 28 oval, peach tablets.

PREMPRO 0.625 mg/5 mg

NDC 0046-1108-11, carton includes 1 blister card containing 28 oval, light-blue tablets.

PREMPHASE therapy consists of two separate tablets; one maroon Premarin tablet taken daily on days 1 through 14 and one light-blue tablet taken on days 15 through 28.

NDC 0046-2575-12, carton includes 1 blister card containing 28 tablets (14 oval, maroon Premarin tablets and 14 oval, light-blue tablets).

The appearance of PREMPRO tablets is a trademark of Pfizer Inc.

The appearance of PREMARIN tablets is a trademark of Pfizer Inc. The appearance of the conjugated estrogens/medroxyprogesterone acetate combination tablets is a trademark.

16.2 Storage and Handling

Store at 20° to 25°C (68° to 77°F); excursions permitted to 15° to 30°C (59° to 86°F) [see USP Controlled Room Temperature].

17 PATIENT COUNSELING INFORMATION

Advise the patients to read the FDA-approved Patient Labeling (Patient Information).

17.1 Abnormal Vaginal Bleeding

Inform postmenopausal women of the importance of reporting abnormal vaginal bleeding to their healthcare provider as soon as possible [see Warnings and Precautions (5.2)].

17.2 Possible Serious Adverse Reactions with Estrogen Plus Progestin Therapy

Inform postmenopausal women of possible serious adverse reactions of estrogen plus progestin therapy including Cardiovascular Disorders, Malignant Neoplasms, and Probable Dementia [see Warnings and Precautions (5.1, 5.2, 5.3)].

17.3 Possible Less Serious but Common Adverse Reactions with Estrogen Plus Progestin Therapy

Inform postmenopausal women of possible less serious but common adverse reactions of estrogen plus progestin therapy such as headache, breast pain and tenderness, nausea and vomiting.

This product's labeling may have been updated. For the most recent prescribing information, please visit www.pfizer.com.

LAB-0502-11.0

PATIENT INFORMATION

PREMPRO®
(Conjugated Estrogens/Medroxyprogesterone Acetate Tablets)
PREMPHASE®
(Conjugated Estrogens plus Medroxyprogesterone Acetate Tablets)

Read this PATIENT INFORMATION before you start taking PREMPRO or PREMPHASE and read what you get each time you refill your PREMPRO or PREMPHASE prescription. There may be new information. This information does not take the place of talking to your healthcare provider about your medical condition or your treatment.

What is the most important information I should know about PREMPRO and PREMPHASE (combinations of estrogens and a progestin)?

- Do not use estrogens with progestins to prevent heart disease, heart attacks, strokes, or dementia (decline of brain function)
- Using estrogens with progestins may increase your chances of getting heart attacks, strokes, breast cancer, or blood clots
- Using estrogens with progestins may increase your chance of getting dementia, based on a study of women 65 years of age or older
- Do not use estrogen-alone to prevent heart disease, heart attacks, strokes or dementia
- Using estrogen-alone may increase your chance of getting cancer of the uterus (womb)
- Using estrogen-alone may increase your chances of getting strokes or blood clots
- Using estrogen-alone may increase your chance of getting dementia, based on a study of women 65 years of age or older
- You and your healthcare provider should talk regularly about whether you still need treatment with PREMPRO or PREMPHASE

What is PREMPRO or PREMPHASE?

PREMPRO or PREMPHASE are medicines that contain two kinds of hormones, estrogens and a progestin.

What is PREMPRO or PREMPHASE used for?

PREMPRO or PREMPHASE is used after menopause to:

- Reduce moderate to severe hot flushes
  Estrogens are hormones made by a woman's ovaries. The ovaries normally stop making estrogens when a woman is between 45 and 55 years old. This drop in body estrogen levels causes the "change of life" or menopause (the end of monthly menstrual periods). Sometimes, both ovaries are removed during an operation before natural menopause takes place. The sudden drop in estrogen levels causes "surgical menopause."
  When the estrogen levels begin dropping, some women get very uncomfortable symptoms, such as feelings of warmth in the face, neck, and chest, or sudden strong feelings of heat and sweating ("hot flushes"). In some women the symptoms are mild, and they will not need to take estrogens. In other women, symptoms can be more severe.
- Treat menopausal changes in and around the vagina
  You and your healthcare provider should talk regularly about whether you still need treatment with PREMPRO or PREMPHASE to control these problems. If you use PREMPRO or PREMPHASE only to treat your menopausal changes in and around your vagina, talk with your healthcare provider about whether a topical vaginal product would be better for you.
- Help reduce your chances of getting osteoporosis (thin weak bones)
  Osteoporosis from menopause is a thinning of the bones that makes them weaker and easier to break. If you use PREMPRO or PREMPHASE only to prevent osteoporosis due to menopause, talk with your healthcare provider about whether a different treatment or medicine without estrogens might be better for you. Weight-bearing exercise, like walking or running, and taking calcium (1500 mg per day of elemental calcium) and vitamin D (400–800 IU per day) supplements may also lower your chances of getting postmenopausal osteoporosis. It is important to talk about exercise and supplements with your healthcare provider before starting them.
  You and your healthcare provider should talk regularly about whether you still need treatment with PREMPRO or PREMPHASE.

Who should not take PREMPRO or PREMPHASE?

Do not take PREMPRO or PREMPHASE if you have had your uterus (womb) removed (hysterectomy).

PREMPRO and PREMPHASE contain a progestin to decrease the chance of getting cancer of the uterus. If you do not have a uterus, you do not need a progestin and you should not take PREMPRO or PREMPHASE.

Do not take PREMPRO or PREMPHASE if you:

- Have unusual vaginal bleeding
- Currently have or have had certain cancers
  Estrogens may increase the chance of getting certain types of cancers, including cancer of the breast or uterus. If you have or have had cancer, talk with your healthcare provider about whether you should use PREMPRO or PREMPHASE.
- Had a stroke or heart attack
- Currently have or have had blood clots
- Currently have or have had liver problems
- Have been diagnosed with a bleeding disorder
- Are allergic to PREMPRO or PREMPHASE or any of their ingredients
  See the list of ingredients in PREMPRO and PREMPHASE at the end of this leaflet.

Tell your healthcare provider

- If you have any unusual vaginal bleeding
  Vaginal bleeding after menopause may be a warning sign of cancer of the uterus (womb). Your healthcare provider should check any unusual vaginal bleeding to find out the cause.
- About all of your medical problems
  Your healthcare provider may need to check you more carefully if you have certain conditions, such as asthma (wheezing), epilepsy (seizures), diabetes, migraine, endometriosis, lupus, problems with your heart, liver, thyroid, kidneys, or have high calcium levels in your blood.
- About all the medicines you take
  This includes prescription and nonprescription medicines, vitamins, and herbal supplements. Some medicines may affect how PREMPRO or PREMPHASE works. PREMPRO or PREMPHASE may also affect how your other medicines work.
- If you are going to have surgery or will be on bedrest
  You may need to stop taking PREMPRO or PREMPHASE.
- If you are pregnant or think you may be pregnant
  PREMPRO and PREMPHASE are not for pregnant women.
- If you are breastfeeding
  The hormones in PREMPRO and PREMPHASE can pass into your breast milk.

How should I take PREMPRO or PREMPHASE?

- Take one PREMPRO or PREMPHASE tablet at the same time each day
- If you miss a dose, take it as soon as possible
  If it is almost time for your next dose, skip the missed dose and go back to your normal schedule. Do not take 2 doses at the same time.
- Estrogens should be used at the lowest dose possible for your treatment only as long as needed
  You and your healthcare provider should talk regularly (for example, every 3 to 6 months) about the dose you are taking and whether you still need treatment with PREMPRO or PREMPHASE.

What are the possible side effects of PREMPRO or PREMPHASE?

Side effects are grouped by how serious they are and how often they happen when you are treated.

Serious, but less common side effects include:

- Heart attack
- Stroke
- Blood clots
- Breast cancer
- Cancer of the lining of the uterus (womb)
- Cancer of the ovary
- Dementia
- High or low blood calcium
- Gallbladder disease
- Visual abnormalities
- High blood pressure
- High levels of fat (triglycerides) in your blood
- Liver problems
- Changes in your thyroid hormone levels
- Fluid retention
- Cancer changes of endometriosis
- Enlargement of benign tumors of the uterus ("fibroids")
- Severe allergic reactions
- Changes in certain laboratory test results, such as high blood sugar

Call your healthcare provider right away if you get any of the following warning signs or any other unusual symptoms that concern you:

- New breast lumps
- Unusual vaginal bleeding
- Changes in vision or speech
- Sudden new severe headaches
- Severe pains in your chest or legs with or without shortness of breath, weakness and fatigue
- Swelling of the face, lips, and tongue with or without red itchy bumps

Common side effects of PREMPRO or PREMPHASE include:

- Headache
- Breast pain
- Irregular vaginal bleeding or spotting
- Stomach or abdominal cramps, bloating
- Nausea and vomiting
- Hair loss
- Fluid retention
- Vaginal yeast infection

These are not all the possible side effects of PREMPRO or PREMPHASE. For more information, ask your healthcare provider or pharmacist for advice about side effects. You may report side effects to Pfizer Inc. at 1-800-438-1985 or to FDA at 1-800-FDA-1088.

What can I do to lower my chances of getting a serious side effect with PREMPRO or PREMPHASE?

- Talk with your healthcare provider regularly about whether you should continue taking PREMPRO or PREMPHASE
- See your healthcare provider right away if you get vaginal bleeding while taking PREMPRO or PREMPHASE
- Have a pelvic exam, breast exam and mammogram (breast X-ray) every year unless your healthcare provider tells you something else
  If members of your family have had breast cancer or if you have ever had breast lumps or an abnormal mammogram, you may need to have breast exams more often.
- If you have high blood pressure, high cholesterol (fat in the blood), diabetes, are overweight, or if you use tobacco, you may have higher chances for getting heart disease
  Ask your healthcare provider for ways to lower your chances of getting heart disease.

General Information about the safe and effective use of PREMPRO and PREMPHASE

Medicines are sometimes prescribed for conditions that are not mentioned in patient information leaflets. Do not take PREMPRO or PREMPHASE for conditions for which it was not prescribed. Do not give PREMPRO or PREMPHASE to other people, even if they have the same symptoms you have. It may harm them.

Keep PREMPRO and PREMPHASE out of the reach of children.

This leaflet provides a summary of the most important information about PREMPRO and PREMPHASE. If you would like more information, talk with your healthcare provider or pharmacist. You can ask for information about PREMPRO and PREMPHASE that is written for health professionals.

What are the ingredients in PREMPRO and PREMPHASE?

PREMPRO contains the same conjugated estrogens found in Premarin, which are a mixture of sodium estrone sulfate and sodium equilin sulfate and other components, including sodium sulfate conjugates, 17α-dihydroequilin, 17α-estradiol and 17β-dihydroequilin. PREMPRO also contains either 1.5, 2.5, or 5 mg of medroxyprogesterone acetate.

PREMPRO 0.3 mg/1.5 mg and 0.45 mg/1.5 mg tablets also contain calcium phosphate tribasic, microcrystalline cellulose, lactose monohydrate, carnauba wax, hypromellose, magnesium stearate, polyethylene glycol, sucrose, hydroxypropyl cellulose, Eudragit NE 30D, titanium dioxide, yellow iron oxide, propylene glycol and black iron oxide.

PREMPRO 0.625 mg/2.5 mg tablets also contain calcium phosphate tribasic, microcrystalline cellulose, carnauba wax, lactose monohydrate, hypromellose, magnesium stearate, polyethylene glycol, sucrose, hydroxypropyl cellulose, Eudragit NE 30D, propylene glycol, titanium dioxide, red iron oxide, yellow iron oxide, and black iron oxide.

PREMPRO 0.625 mg/5 mg tablets also contain calcium phosphate tribasic, carnauba wax, Eudragit NE 30D, hydroxypropyl cellulose, hypromellose, lactose monohydrate, magnesium stearate, microcrystalline cellulose, polyethylene glycol, sucrose, titanium dioxide, triethyl citrate, FD&C Blue No. 2, black iron oxide, and propylene glycol.

PREMPHASE is two separate tablets. One tablet (maroon color) is 0.625 mg of Premarin, which is a mixture of sodium estrone sulfate and sodium equilin sulfate and other components, including sodium sulfate conjugates, 17 α-dihydroequilin, 17 α-estradiol and 17 β-dihydroequilin. The maroon tablet also contains calcium phosphate tribasic, carnauba wax, hydroxypropyl cellulose, microcrystalline cellulose, powdered cellulose, hypromellose, lactose monohydrate, magnesium stearate, polyethylene glycol, sucrose, titanium dioxide, propylene glycol, FD&C Blue No. 2, FD&C Red No. 40. The second tablet (light-blue color) contains 0.625 mg of the same ingredients as the maroon color tablet plus 5 mg of medroxyprogesterone acetate. The light-blue tablet also contains calcium phosphate tribasic, carnauba wax, Eudragit NE 30D, hydroxypropyl cellulose, hypromellose, lactose monohydrate, magnesium stearate, microcrystalline cellulose, polyethylene glycol, sucrose, titanium dioxide, triethyl citrate, FD&C Blue No. 2, black iron oxide, and propylene glycol.

PREMPRO therapy consists of a single tablet to be taken once daily.

PREMPRO 0.3 mg/1.5 mg

Blister Card - Each carton includes 1 blister card containing 28 oval, cream tablets. Each tablet contains 0.3 mg of the conjugated estrogens found in Premarin tablets and 1.5 mg of medroxyprogesterone acetate for oral administration.

PREMPRO 0.45 mg/1.5 mg

Blister Card - Each carton includes 1 blister card containing 28 oval, gold tablets. Each tablet contains 0.45 mg of the conjugated estrogens found in Premarin tablets and 1.5 mg of medroxyprogesterone acetate for oral administration.

PREMPRO 0.625 mg/2.5 mg

Blister Card - Each carton includes 1 blister card containing 28 oval, peach tablets. Each tablet contains 0.625 mg of the conjugated estrogens found in Premarin tablets and 2.5 mg of medroxyprogesterone acetate for oral administration.

PREMPRO 0.625 mg/5 mg

Blister Card - Each carton includes 1 blister card containing 28 oval, light-blue tablets. Each tablet contains 0.625 mg of the conjugated estrogens found in Premarin tablets and 5 mg of medroxyprogesterone acetate for oral administration.

PREMPHASE therapy consists of two separate tablets; one maroon Premarin tablet taken daily on days 1 through 14 and one light-blue tablet taken on days 15 through 28.

Each carton includes 1 blister pack containing 28 tablets. One blister pack contains 14 oval, maroon Premarin tablets containing 0.625 mg of conjugated estrogens and 14 oval, light-blue tablets that contain 0.625 mg of the conjugated estrogens found in Premarin tablets and 5 mg of medroxyprogesterone acetate for oral administration.

The appearance of PREMPRO tablets is a trademark of Pfizer Inc.

The appearance of PREMARIN tablets is a trademark of Pfizer Inc. The appearance of the conjugated estrogens/medroxyprogesterone acetate combination tablets is a trademark.

Store at 20° to 25°C (68° to 77°F); excursions permitted to 15° to 30°C (59° to 86°F) [see USP Controlled Room Temperature].

This product's labeling may have been updated. For the most recent prescribing information, please visit www.pfizer.com.

LAB-0504-11.0
Revised 04/2025

PRINCIPAL DISPLAY PANEL - 28 Tablet 0.625 mg / 5 mg Blister Pack

START HERE
Rx only
NDC 0046-2575-12

DAY 1 → DAY 2 → DAY 3 → DAY 4 → DAY 5 → DAY 6 → DAY 7

14 maroon tablets of 0.625 mg conjugated estrogens

DAY 14 ← DAY 13 ← DAY 12 ← DAY 11 ← DAY 10 ← DAY 9 ← DAY 8

PREMPHASE® (conjugated estrogens/medroxyprogesterone acetate tablets)

DAY 15 → DAY 16 → DAY 17 → DAY 18 → DAY 19 → DAY 20 → DAY 21

14 light-blue tablets of 0.625 mg conjugated estrogens/5 mg medroxyprogesterone acetate

DAY 28 ← DAY 27 ← DAY 26 ← DAY 25 ← DAY 24 ← DAY 23 ← DAY 22

PRINCIPAL DISPLAY PANEL - Kit Carton

NDC 0046-2575-12

Pfizer

PREMPHASE®
(conjugated estrogens/medroxyprogesterone
acetate tablets)

14 maroon tablets of 0.625 mg conjugated estrogens

14 light-blue tablets of 0.625 mg conjugated estrogens/
5 mg medroxyprogesterone acetate

Package contains 1 blister card
of 28 tablets

Rx only

PRINCIPAL DISPLAY PANEL - 0.3 mg / 1.5 mg Blister Card

28 Tablets
NDC 0046-1105-11

WEEK 1
WEEK 2
WEEK 3
WEEK 4

Pfizer

PREMPRO®
(conjugated estrogens/medroxyprogesterone acetate tablets)

0.3 mg / 1.5 mg

Each cream tablet contains 0.3 mg of Premarin® brand of
conjugated estrogens and 1.5 mg of medroxyprogesterone acetate.

Directions for Use: Take one tablet each day until all tablets
have been taken. See accompanying information.

Store at 20° to 25°C (68° to 77°F); excursions permitted
to 15° to 30°C (59° to 86°F).
[See USP Controlled Room Temperature]

Note: Package not child resistant. Keep this and all
medications out of the reach of children.

PREMPRO 0.3 mg/1.5 mg

Distributed by
Wyeth Pharmaceuticals LLC
A subsidiary of Pfizer Inc.
Philadelphia, PA 19101

www.PREMPRO.com

Rx only

PAA224096

WEEK 1
WEEK 2
WEEK 3
WEEK 4

LOT XXXXXXX
EXP YYYY-MMM

PRINCIPAL DISPLAY PANEL - 0.3 mg / 1.5 mg Blister Card Carton

NDC 0046-1105-11

Pfizer

PREMPRO®
(conjugated estrogens/
medroxyprogesterone
acetate tablets)

0.3 mg / 1.5 mg

Package contains 1 blister card of 28 tablets.

www.PREMPRO.com
Rx only

PRINCIPAL DISPLAY PANEL - 0.45 mg / 1.5 mg Blister Card

28 Tablets
NDC 0046-1106-11

WEEK 1
WEEK 2
WEEK 3
WEEK 4

Pfizer

PREMPRO®
(conjugated estrogens/medroxyprogesterone acetate tablets)

0.45 mg / 1.5 mg

Each gold tablet contains 0.45 mg of Premarin® brand of conjugated estrogens
and 1.5 mg of medroxyprogesterone acetate.

Directions for Use: Take one tablet each day until all tablets
have been taken. See accompanying information.

Store at 20° to 25°C (68° to 77°F); excursions permitted
to 15° to 30°C (59° to 86°F).
[See USP Controlled Room Temperature]

Note: Package not child resistant. Keep this and all
medications out of the reach of children.

PREMPRO 0.45 mg/1.5 mg

Distributed by
Wyeth Pharmaceuticals LLC
A subsidiary of Pfizer Inc.
Philadelphia, PA 19101

www.PREMPRO.com

Rx only

PAA224094

WEEK 1
WEEK 2
WEEK 3
WEEK 4

LOT XXXXXXX
EXP YYYY-MMM

PRINCIPAL DISPLAY PANEL - 0.45 mg / 1.5 mg Blister Card Carton

NDC 0046-1106-11

Pfizer

PREMPRO®
(conjugated estrogens/
medroxyprogesterone
acetate tablets)

0.45 mg / 1.5 mg

Package contains 1 blister card of 28 tablets.

www.PREMPRO.com
Rx only

PRINCIPAL DISPLAY PANEL - 0.625 mg / 2.5 mg Tablet Blister Card

28 Tablets
NDC 0046-1107-11

WEEK 1
WEEK 2
WEEK 3
WEEK 4

Pfizer

PREMPRO®
(conjugated estrogens/medroxyprogesterone acetate tablets)

0.625 mg / 2.5 mg

Each peach tablet contains 0.625 mg of Premarin® brand of
conjugated estrogens and 2.5 mg of medroxyprogesterone acetate.

Directions for Use: Take one tablet each day until all tablets
have been taken. See accompanying information.

Store at 20° to 25°C (68° to 77°F); excursions permitted
to 15° to 30°C (59° to 86°F).
[See USP Controlled Room Temperature]

Note: Package not child resistant. Keep this and all
medications out of the reach of children.

MADE IN IRELAND

PREMPRO 0.625 mg/2.5 mg

Distributed by
Wyeth Pharmaceuticals LLC
A subsidiary of Pfizer Inc.
Philadelphia, PA 19101

Rx only

www.PREMPRO.com

PAA224092

WEEK 1
WEEK 2
WEEK 3
WEEK 4

LOT XXXXXXX
EXP YYYY-MMM

PRINCIPAL DISPLAY PANEL - 0.625 mg / 2.5 mg Tablet Blister Card Carton

NDC 0046-1107-11

Pfizer
PREMPRO®
(conjugated estrogens/
medroxyprogesterone acetate tablets)

0.625 mg / 2.5 mg

Rx only

Package contains 1 blister card of 28 tablets.
www.PREMPRO.com

PRINCIPAL DISPLAY PANEL - 0.625 mg / 5 mg Tablet Blister Card

28 Tablets
NDC 0046-1108-11

WEEK 1
WEEK 2
WEEK 3
WEEK 4

Pfizer

PREMPRO®
(conjugated estrogens/medroxyprogesterone acetate tablets)

Rx only

0.625 mg / 5 mg

Each light-blue tablet contains 0.625 mg of Premarin® brand of
conjugated estrogens and 5 mg of medroxyprogesterone acetate.

Directions for Use: Take one tablet each day until all tablets
have been taken. See accompanying information.

Store at 20° to 25°C (68° to 77°F); excursions permitted
to 15° to 30°C (59° to 86°F).
[See USP Controlled Room Temperature]

Note: Package not child resistant. Keep this and all
medications out of the reach of children.

MADE IN IRELAND

PREMPRO 0.625 mg/5 mg

Distributed by
Wyeth Pharmaceuticals LLC
A subsidiary of Pfizer Inc.
Philadelphia, PA 19101

www.PREMPRO.com

PAA224000

WEEK 1
WEEK 2
WEEK 3
WEEK 4

LOT XXXXXXX
EXP YYYY-MMM

PRINCIPAL DISPLAY PANEL - 0.625 mg / 5 mg Tablet Blister Card Carton

NDC 0046-1108-11

Rx only

Pfizer
PREMPRO®
(conjugated estrogens/
medroxyprogesterone acetate tablets)

0.625 mg / 5 mg

Package contains 1 blister card of 28 tablets.
www.PREMPRO.com